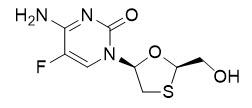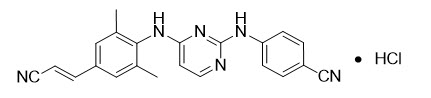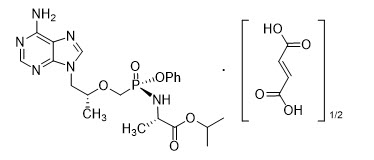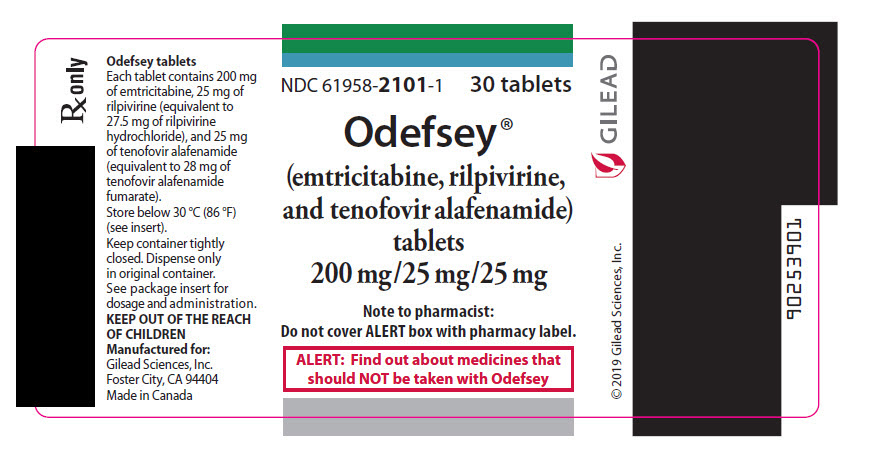 DRUG LABEL: ODEFSEY
NDC: 61958-2101 | Form: TABLET
Manufacturer: Gilead Sciences, Inc.
Category: prescription | Type: HUMAN PRESCRIPTION DRUG LABEL
Date: 20251202

ACTIVE INGREDIENTS: EMTRICITABINE 200 mg/1 1; RILPIVIRINE HYDROCHLORIDE 25 mg/1 1; TENOFOVIR ALAFENAMIDE FUMARATE 25 mg/1 1
INACTIVE INGREDIENTS: LACTOSE MONOHYDRATE; MICROCRYSTALLINE CELLULOSE; POVIDONE, UNSPECIFIED; POLYSORBATE 20; CROSCARMELLOSE SODIUM; MAGNESIUM STEARATE; WATER; POLYVINYL ALCOHOL, UNSPECIFIED; TITANIUM DIOXIDE; POLYETHYLENE GLYCOL, UNSPECIFIED; TALC; FERROSOFERRIC OXIDE

HIGHLIGHTS OF PRESCRIBING INFORMATION

These highlights do not include all the information needed to use ODEFSEY safely and effectively. See full prescribing information for ODEFSEY.
ODEFSEY® (emtricitabine, rilpivirine, and tenofovir alafenamide) tablets, for oral use
Initial U.S. Approval: 2016

WARNING: POST TREATMENT ACUTE EXACERBATION OF HEPATITIS B

See full prescribing information for complete boxed warning.

Severe acute exacerbations of hepatitis B have been reported in patients with HIV-1 and HBV who have discontinued products containing emtricitabine (FTC) and/or tenofovir disoproxil fumarate (TDF), and may occur with discontinuation of ODEFSEY. Hepatic function should be monitored closely in these patients. If appropriate, anti-hepatitis B therapy may be warranted. (5.1)

RECENT MAJOR CHANGES

Indications and Usage (1) | 02/2025
Dosage and Administration (2.2) | 02/2025

1 INDICATIONS AND USAGE

ODEFSEY is a three-drug combination of emtricitabine (FTC) and tenofovir alafenamide (TAF), both HIV nucleoside analog reverse transcriptase inhibitors (NRTIs), and rilpivirine (RPV), a non-nucleoside reverse transcriptase inhibitor (NNRTI), and is indicated as a complete regimen for the treatment of HIV-1 infection in adult and pediatric patients weighing at least 25kg:

- as initial therapy in those with no antiretroviral treatment history with HIV-1 RNA less than or equal to 100,000 copies/mL; or
- to replace a stable antiretroviral regimen in those who are virologically-suppressed (HIV-1 RNA less than 50 copies/mL) for at least 6 months with no history of treatment failure and no known substitutions associated with resistance to the individual components of ODEFSEY. (1)

Limitations of Use:

- More rilpivirine-treated participants with HIV-1 RNA greater than 100,000 copies/mL at the start of therapy experienced virologic failure (HIV-1 RNA ≥ 50 copies/mL) compared to rilpivirine-treated participants with HIV-1 RNA less than or equal to 100,000 copies/mL. (14.2,14.3)

2 DOSAGE AND ADMINISTRATION

- Testing: Prior to or when initiating ODEFSEY, test for hepatitis B virus infection. Prior to or when initiating ODEFSEY, and during treatment on a clinically appropriate schedule, assess serum creatinine, estimated creatinine clearance, urine glucose, and urine protein in all patients. In patients with chronic kidney disease, also assess serum phosphorus (2.1)
- Recommended dosage: one tablet taken orally once daily with a meal. (2.2)
- For pregnant patients who are already on ODEFSEY prior to pregnancy and who are virologically suppressed (HIV-1 RNA less than 50 copies per mL), one tablet taken once daily may be continued. Lower exposures of rilpivirine were observed during pregnancy, therefore viral load should be monitored closely. (2.3)
- Renal impairment: ODEFSEY is not recommended in patients with estimated creatinine clearance of 15 to below 30 mL per minute, or below 15 mL per minute who are not receiving chronic hemodialysis. (2.4)

3 DOSAGE FORMS AND STRENGTHS

Tablets: 200 mg of FTC, 25 mg of RPV and 25 mg of TAF. (3)

4 CONTRAINDICATIONS

ODEFSEY is contraindicated when coadministered with drugs where significant decreases in RPV plasma concentrations may occur, which may result in loss of virologic response and possible resistance and cross-resistance. (4)

5 WARNINGS AND PRECAUTIONS

- Skin and Hypersensitivity Reactions: Severe skin and hypersensitivity reactions have been reported during postmarketing experience with RPV-containing regimens, including cases of Drug Reaction with Eosinophilia and Systemic Symptoms (DRESS). Immediately discontinue treatment if hypersensitivity or rash with systemic symptoms or elevations in hepatic serum biochemistries develops and closely monitor clinical status, including hepatic serum biochemistries. (5.2)
- Hepatotoxicity: Hepatic adverse events have been reported in patients receiving an RPV-containing regimen. Monitor liver-associated tests before and during treatment with ODEFSEY in patients with underlying hepatic disease or marked elevations in liver-associated tests. Also consider monitoring liver-associated tests in patients without risk factors. (5.3)
- Depressive disorders: Severe depressive disorders have been reported. Immediate medical evaluation is recommended for severe depressive disorders. (5.4)
- New onset or worsening renal impairment: Assessment of serum creatinine, estimated creatinine clearance, urine glucose, and urine protein when initiating ODEFSEY and during therapy on a clinically appropriate schedule in all patients. Also assess serum phosphorus in patients with chronic kidney disease. (5.5)
- Concomitant use of ODEFSEY with drugs with a known risk to prolong the QTc interval of the electrocardiogram may increase the risk of Torsade de Pointes. (5.6)
- Lactic acidosis/severe hepatomegaly with steatosis: Discontinue treatment in patients who develop symptoms or laboratory findings suggestive of lactic acidosis or pronounced hepatotoxicity. (5.7)
- Immune reconstitution syndrome: May necessitate further evaluation and treatment. (5.8)

6 ADVERSE REACTIONS

Most common adverse reactions (incidence greater than or equal to 2%, all grades) are headache and sleep disturbances. (6.1)

To report SUSPECTED ADVERSE REACTIONS, contact Gilead Sciences, Inc. at 1-800-GILEAD-5 or FDA at 1-800-FDA-1088 or www.fda.gov/medwatch.

7 DRUG INTERACTIONS

- ODEFSEY is a complete regimen for the treatment of HIV-1 infection; therefore, coadministration with other antiretroviral medications for the treatment of HIV-1 infection is not recommended. (7.1)
- Consult the Full Prescribing Information prior to and during treatment for important drug interactions. (4, 5.6, 7)

8 USE IN SPECIFIC POPULATIONS

- Pregnancy: Total rilpivirine exposures were generally lower during pregnancy compared to the postpartum period. (2.3, 8.1, 12.3).
- Pediatrics: Not recommended for patients weighing less than 25 kg. (8.4)

FULL PRESCRIBING INFORMATION

WARNING: POST TREATMENT ACUTE EXACERBATION OF HEPATITIS B

Severe acute exacerbations of hepatitis B have been reported in patients with HIV-1 and HBV who have discontinued products containing emtricitabine (FTC) and/or tenofovir disoproxil fumarate (TDF), and may occur with discontinuation of ODEFSEY.

Hepatic function should be monitored closely with both clinical and laboratory follow-up for at least several months in patients with HIV-1 and HBV who discontinue ODEFSEY. If appropriate, anti-hepatitis B therapy may be warranted [see Warnings and Precautions (5.1)].

1 INDICATIONS AND USAGE

ODEFSEY is indicated as a complete regimen for the treatment of HIV-1 infection in adult and pediatric patients weighing at least 25 kg:

- as initial therapy in those with no antiretroviral treatment history with HIV-1 RNA less than or equal to 100,000 copies/mL or
- to replace a stable antiretroviral regimen in those who are virologically-suppressed (HIV-1 RNA less than 50 copies/mL) for at least 6 months with no history of treatment failure and no known substitutions associated with resistance to the individual components of ODEFSEY [see Microbiology (12.4) and Clinical Studies (14)].

Limitations of Use:

- More rilpivirine-treated participants with no antiretroviral treatment history with HIV-1 RNA greater than 100,000 copies/mL at the start of therapy experienced virologic failure (HIV-1 RNA ≥ 50 copies/mL) compared to rilpivirine-treated participants with HIV-1 RNA less than or equal to 100,000 copies/mL [see Clinical Studies (14.2,14.3)].

2 DOSAGE AND ADMINISTRATION

2.1 Testing Prior to Initiation and During Treatment with ODEFSEY

Prior to or when initiating ODEFSEY, test patients for hepatitis B virus infection [see Warnings and Precautions (5.1)].

Prior to or when initiating ODEFSEY, and during treatment with ODEFSEY, on a clinically appropriate schedule, assess serum creatinine, estimated creatinine clearance, urine glucose, and urine protein in all patients. In patients with chronic kidney disease, also assess serum phosphorus [see Warnings and Precautions (5.5)].

2.2 Recommended Dosage in Adult and Pediatric Patients Weighing at Least 25 kg

ODEFSEY is a three-drug fixed dose combination product containing 200 mg of emtricitabine (FTC), 25 mg of rilpivirine (RPV), and 25 mg of tenofovir alafenamide (TAF). The recommended dosage of ODEFSEY is one tablet taken orally once daily with a meal in adults and pediatric patients with body weight at least 25 kg and creatinine clearance greater than or equal to 30 mL per minute [see Use in Specific Populations (8.6) and Clinical Pharmacology (12.3)].

2.3 Recommended Dosage During Pregnancy

For pregnant patients who are already on ODEFSEY prior to pregnancy and are virologically suppressed (HIV-1 RNA less than 50 copies per mL), one tablet of ODEFSEY taken once daily may be continued. Lower exposures of rilpivirine, a component of ODEFSEY, were observed during pregnancy, therefore viral load should be monitored closely [see Use in Specific Populations (8.1) and Clinical Pharmacology (12.3)].

2.4 Not Recommended in Patients with Severe Renal Impairment

ODEFSEY is not recommended in patients with:

- severe renal impairment (estimated creatinine clearance of 15 to below 30 mL per minute); or
- end stage renal disease (ESRD; estimated creatinine clearance below 15 mL per minute) who are not receiving chronic hemodialysis [see Dosage and Administration (2.2), Warnings and Precautions (5.5), and Use in Specific Populations (8.6)].

3 DOSAGE FORMS AND STRENGTHS

Each ODEFSEY tablet contains 200 mg of emtricitabine (FTC), 25 mg of rilpivirine (RPV) (equivalent to 27.5 mg of rilpivirine hydrochloride), and 25 mg of tenofovir alafenamide (TAF) (equivalent to 28 mg of tenofovir alafenamide fumarate).

The tablets are gray, capsule-shaped, film-coated and debossed with "GSI" on one side and "255" on the other side.

4 CONTRAINDICATIONS

ODEFSEY is contraindicated when coadministered with the following drugs; coadministration may result in loss of virologic response and possible resistance to ODEFSEY or to the class of NNRTIs [see Warnings and Precautions (5.6), Drug Interactions (7) and Clinical Pharmacology (12.3)]:

- Anticonvulsants: carbamazepine, oxcarbazepine, phenobarbital, phenytoin
- Antimycobacterials: rifampin, rifapentine
- Glucocorticoid (systemic): dexamethasone (more than a single-dose)
- Herbal Products: St. John's wort (Hypericum perforatum)
- Proton Pump Inhibitors: e.g., dexlansoprazole, esomeprazole, lansoprazole, omeprazole, pantoprazole, rabeprazole

5 WARNINGS AND PRECAUTIONS

5.1 Severe Acute Exacerbation of Hepatitis B in Patients with HIV-1 and HBV

Test patients with HIV-1 for the presence of hepatitis B virus (HBV) before or when initiating antiretroviral therapy [see Dosage and Administration (2.1)].

Severe acute exacerbations of hepatitis B (e.g., liver decompensation and liver failure) have been reported in patients with HIV-1 and HBV who have discontinued products containing FTC and/or TDF, and may occur with discontinuation of ODEFSEY. Patients with HIV-1 and HBV who discontinue ODEFSEY should be closely monitored with both clinical and laboratory follow-up for at least several months after stopping treatment with ODEFSEY. If appropriate, anti-hepatitis B therapy may be warranted, especially in patients with advanced liver disease or cirrhosis, since post treatment exacerbation of hepatitis may lead to hepatic decompensation and liver failure.

5.2 Skin and Hypersensitivity Reactions

Severe skin and hypersensitivity reactions, including cases of Drug Reaction with Eosinophilia and Systemic Symptoms (DRESS), have been reported during postmarketing experience with RPV-containing regimens. While some skin reactions were accompanied by constitutional symptoms such as fever, other skin reactions were associated with organ dysfunction, including elevations in hepatic serum biochemistries. During Phase 3 clinical trials of RPV, treatment-related rashes with at least Grade 2 severity were reported in 1% of participants. Overall, most rashes were Grade 1 or 2 and occurred in the first four to six weeks of therapy [see Adverse Reactions (6.2)].

Discontinue ODEFSEY immediately if signs or symptoms of severe skin or hypersensitivity reactions develop, including but not limited to, severe rash or rash accompanied by fever, blisters, mucosal involvement, conjunctivitis, facial edema, angioedema, hepatitis, or eosinophilia. Clinical status including laboratory parameters should be monitored and appropriate therapy should be initiated.

5.3 Hepatotoxicity

Hepatic adverse events have been reported in patients receiving an RPV-containing regimen. Patients with underlying hepatitis B or C virus infection, or marked elevations in liver-associated tests prior to treatment, may be at increased risk for worsening or development of liver-associated test elevations with use of ODEFSEY. A few cases of hepatic toxicity have been reported in adult patients receiving an RPV-containing regimen who had no preexisting hepatic disease or other identifiable risk factors. Appropriate laboratory testing prior to initiating therapy and monitoring for hepatotoxicity during therapy with ODEFSEY is recommended in patients with underlying hepatic disease such as hepatitis B or C, or in patients with marked elevations in liver-associated tests prior to treatment initiation. Liver-associated test monitoring should also be considered for patients without preexisting hepatic dysfunction or other risk factors.

5.4 Depressive Disorders

Depressive disorders (including depressed mood, depression, dysphoria, major depression, mood altered, negative thoughts, suicide attempt, suicidal ideation) have been reported with RPV. Promptly evaluate patients with severe depressive symptoms to assess whether the symptoms are related to ODEFSEY, and to determine whether the risks of continued therapy outweigh the benefits.

In Phase 3 trials of RPV in adult participants (N=1368) through 96 weeks, the incidence of depressive disorders (regardless of causality, severity) reported among RPV-treated participants (n=686) was 9%. Most events were mild or moderate in severity. In RPV-treated participants, the incidence of Grades 3 and 4 depressive disorders (regardless of causality) was 1%, the incidence of discontinuation due to depressive disorders was 1%, and suicidal ideation and suicide attempt was reported in 4 and 2 participants, respectively.

During the Phase 2 trial in RPV-treated pediatric participants 12 to less than 18 years of age (N=36), the incidence of depressive disorders (regardless of causality, severity) was 19% (7/36) through 48 weeks. Most events were mild or moderate in severity. The incidence of Grades 3 and 4 depressive disorders (regardless of causality) was 6% (2/36). None of the participants discontinued due to depressive disorders. Suicidal ideation and suicide attempt were reported in 1 participant.

5.5 New Onset or Worsening Renal Impairment

Postmarketing case of renal impairment, including acute renal failure, proximal renal tubulopathy (PRT), and Fanconi syndrome have been reported with TAF-containing products; while most of these cases were characterized by potential confounders that may have contributed to the reported renal events, it is also possible these factors may have predisposed patients to tenofovir-related adverse events [see Adverse Reactions (6.1, 6.2)]. ODEFSEY is not recommended in patients with estimated creatinine clearance of 15 to below 30 mL per minute, or in patients with estimated creatinine clearance below 15 mL per minute who are not receiving chronic hemodialysis.

Patients taking tenofovir prodrugs who have impaired renal function and those taking nephrotoxic agents, including nonsteroidal anti-inflammatory drugs are at increased risk of developing renal-related adverse reactions.

Prior to or when initiating ODEFSEY, and during treatment with ODEFSEY, on a clinically appropriate schedule, assess serum creatinine, estimated creatinine clearance, urine glucose and urine protein in all patients. In patients with chronic kidney disease, also assess serum phosphorus. Discontinue ODEFSEY in patients who develop clinically significant decreases in renal function or evidence of Fanconi syndrome.

5.6 Risk of Adverse Reactions or Loss of Virologic Response Due to Drug Interactions

The concomitant use of ODEFSEY and other drugs may result in potentially significant drug interactions, some of which may lead to [see Contraindications (4), and Drug Interactions (7)]:

- Loss of therapeutic effect of ODEFSEY and possible development of resistance due to reduced exposure of RPV.

In healthy participants, higher than recommended doses of RPV (75 mg once daily and 300 mg once daily – 3 and 12 times the recommended dosages in ODEFSEY, respectively) have been shown to prolong the QTc interval of the electrocardiogram. Consider alternatives to ODEFSEY when coadministered with a drug that is known to have a risk of Torsade de Pointes [see Drug Interactions (7.2) and Clinical Pharmacology (12.2)].

See Table 3 for steps to prevent or manage these possible and known significant drug interactions, including dosing recommendations [see Contraindications (4) and Drug Interactions (7)]. Consider the potential for drug interactions prior to and during ODEFSEY therapy and review concomitant medications during ODEFSEY therapy.

5.7 Lactic Acidosis/Severe Hepatomegaly with Steatosis

Lactic acidosis and severe hepatomegaly with steatosis, including fatal cases, have been reported with the use of nucleoside analogs, including emtricitabine, a component of ODEFSEY, and tenofovir DF, another prodrug of tenofovir, alone or in combination with other antiretrovirals. Treatment with ODEFSEY should be suspended in any patient who develops clinical or laboratory findings suggestive of lactic acidosis or pronounced hepatotoxicity (which may include hepatomegaly and steatosis even in the absence of marked transaminase elevations).

5.8 Immune Reconstitution Syndrome

Immune reconstitution syndrome has been reported in patients treated with combination antiretroviral therapy, including FTC and RPV, both components of ODEFSEY. During the initial phase of combination antiretroviral treatment, patients whose immune system responds may develop an inflammatory response to indolent or residual opportunistic infections [such as Mycobacterium avium infection, cytomegalovirus, Pneumocystis jirovecii pneumonia (PCP), or tuberculosis], which may necessitate further evaluation and treatment.

Autoimmune disorders (such as Graves' disease, polymyositis, Guillain-Barré syndrome, and autoimmune hepatitis) have also been reported to occur in the setting of immune reconstitution, however, the time to onset is more variable, and can occur many months after initiation of treatment.

6 ADVERSE REACTIONS

The following adverse reactions are discussed in other sections of the labeling:

- Severe Acute Exacerbations of Hepatitis B [see Warnings and Precautions (5.1)]
- Skin and Hypersensitivity Reactions [see Warnings and Precautions (5.2)]
- Hepatotoxicity [see Warnings and Precautions (5.3)]
- Depressive Disorders [see Warnings and Precautions (5.4)]
- New Onset or Worsening Renal Impairment [see Warnings and Precautions (5.5)]
- Lactic Acidosis/Severe Hepatomegaly with Steatosis [see Warnings and Precautions (5.7)]
- Immune Reconstitution Syndrome [see Warnings and Precautions (5.8)]

6.1 Clinical Trials Experience

Because clinical trials are conducted under widely varying conditions, adverse reaction rates observed in the clinical trials of a drug (or a drug given in various combinations with other concomitant therapy) cannot be directly compared to rates in the clinical trials of another drug (or drug given in the same or different combination therapy) and may not reflect the rates observed in practice.

Adverse Reactions in Clinical Trials of ODEFSEY in Virologically-Suppressed Adult Participants with HIV-1

The safety of ODEFSEY in virologically-suppressed adults is based on Week 48 data from two randomized, double-blinded, active-controlled clinical trials, 1160 and 1216, that enrolled 1505 adult participants with HIV-1 who were virologically-suppressed for at least 6 months. Both trials were designed to compare switching to ODEFSEY to maintaining efavirenz/emtricitabine/tenofovir disoproxil fumarate (EFV/FTC/TDF) or emtricitabine/rilpivirine/tenofovir disoproxil fumarate (FTC/RPV/TDF) in Trials 1160 and 1216, respectively. A total of 754 participants received one tablet of ODEFSEY daily [see Clinical Studies (14.1)].

The most common adverse reactions (all Grades) reported in at least 2% of participants in the ODEFSEY group across Trials 1216 and 1160 were headache and sleep disturbances (Table 1). Over 98% of the adverse reactions in the ODEFSEY group were of mild to moderate intensity. The proportion of participants who discontinued treatment with ODEFSEY due to adverse events, regardless of severity, was 2% compared to 1% for FTC/RPV/TDF and 2% for EFV/FTC/TDF.

Table 1 Adverse Reactions [Frequencies of adverse reactions are based on all adverse events attributed to study drugs by the investigator.] (All Grades) Reported in ≥1% of Virologically-Suppressed Adults with HIV-1 in Trial 1160 or Trial 1216 (Week 48 analysis)
Adverse Reaction | Trial 1160 |  | Trial 1216
Adverse Reaction | ODEFSEY (N=438) | EFV/FTC/TDF (N=437) [Data from Trials 1160 and 1216 do not provide an adequate basis for comparison of adverse reaction incidences between ODEFSEY and the FTC/RPV/TDF and EFV/FTC/TDF groups.] | ODEFSEY (N=316) | FTC/RPV/TDF (N=313)
Headache | 2% | 1% | 0 | 1%
Sleep Disturbances | 2% | 1% | 0 | <1%
Flatulence | 1% | <1% | <1% | 1%
Abnormal Dreams | 1% | 1% | 0 | 2%
Diarrhea | 1% | 3% | 1% | 2%
Nausea | 1% | 1% | 1% | 1%

Renal Laboratory Tests

In Trial 1216, the median baseline eGFR was 104 mL per minute for participants who switched to ODEFSEY from FTC/RPV/TDF (N=316) and the mean serum creatinine decreased by 0.02 mg per dL from baseline to Week 48.

In Trial 1160, the median baseline eGFR was 110 mL per minute for participants who switched to ODEFSEY from EFV/FTC/TDF (N=438), and the mean serum creatinine increased by 0.1 mg per dL from baseline to Week 48.

Bone Mineral Density Effects

Changes in BMD from baseline to Week 48 were assessed by dual-energy X-ray absorptiometry (DXA) in Trials 1216 and 1160.

In Trial 1216, mean bone mineral density (BMD) increased in participants who switched to ODEFSEY (1.61% lumbar spine, 1.04% total hip) and remained stable or decreased in participants who remained on FTC/RPV/TDF (0.08% lumbar spine, −0.25% total hip). BMD declines of 5% or greater at the lumbar spine were experienced by 1.7% of ODEFSEY participants and 3.0% of FTC/RPV/TDF participants. BMD declines of 7% or greater at the femoral neck were experienced by 0% of ODEFSEY participants and 1.2% of FTC/RPV/TDF participants.

In Trial 1160, mean BMD increased in participants who switched to ODEFSEY (1.65% lumbar spine, 1.28% total hip) and decreased slightly in participantswho remained on EFV/FTC/TDF (−0.05% lumbar spine, −0.13% total hip). BMD declines of 5% or greater at the lumbar spine were experienced by 2.3% of ODEFSEY participants and 4.9% of EFV/FTC/TDF participants. BMD declines of 7% or greater at the femoral neck were experienced by 1.4% of ODEFSEY participants and 3.3% of EFV/FTC/TDF participants. The long-term clinical significance of these BMD changes is not known.

Serum Lipids

Changes from baseline in total cholesterol, HDL-cholesterol, LDL-cholesterol, triglycerides, and total cholesterol to HDL ratio for Trials 1216 and 1160 are presented in Table 2.

Table 2 Lipid Values, Mean Change from Baseline Reported in Participants Receiving ODEFSEY, FTC/RPV/TDF and EFV/FTC/TDF in Trials 1216 and 1160 at 48 Weeks
 | Trial 1216 |  |  |  | Trial 1160
 | ODEFSEY N=316 [n=235] |  | FTC/RPV/TDF N=314 [n=245] |  | ODEFSEY N=438 [n=295] |  | EFV/FTC/TDF N=437 [n=308]
 | Baseline | Week 48 | Baseline | Week 48 | Baseline | Week 48 | Baseline | Week 48
 | mg/dL | Change [The change from baseline is the mean of within-participant changes from baseline for participants with both baseline and Week 48 values.] , [Participants who received lipid-lowering agents during the treatment period were excluded.] | mg/dL | Change, | mg/dL | Change, | mg/dL | Change,
Total Cholesterol (fasted) | 176 | +17 | 171 | 0 | 193 | -7 | 192 | -3
HDL-Cholesterol (fasted) | 50 | +3 | 48 | 0 | 56 | -4 | 55 | -2
LDL-Cholesterol (fasted) | 111 | +13 | 108 | +1 | 118 [[n=296] for ODEFSEY group in Study 1160 for LDL-Cholesterol (fasted)] | -1 | 119 | -1
Triglycerides (fasted) | 116 | +12 | 119 | -9 | 139 | -12 | 133 | +3
Total Cholesterol to HDL Ratio | 3.7 | +0.2 | 3.8 | +0.1 | 3.7 | +0.2 | 3.8 | 0

Adverse Reactions in Clinical Trials of RPV-Containing Regimens in Treatment-Naïve Adult Participants with HIV-1

In pooled 96-week trials of antiretroviral treatment-naïve adult participants with HIV-1, the most common adverse reactions in participantstreated with RPV+FTC/TDF (N=550) (incidence greater than or equal to 2%, Grades 2−4) were headache, depressive disorders, and insomnia. The proportion of participants who discontinued treatment with RPV+FTC/TDF due to adverse reactions, regardless of severity, was 2%. The most common adverse reactions that led to discontinuation in this treatment group were psychiatric disorders (1.6%) and rash (0.2%). Although the safety profile was similar in virologically-suppressed adults with HIV-1 who were switched to RPV and other antiretroviral drugs, the frequency of adverse events increased by 20% (N=317).

Adrenal Function

In the pooled Phase 3 trials, at Week 96, there was an overall mean change from baseline in basal cortisol of -0.69 (-1.12, 0.27) micrograms/dL in the RPV group and of -0.02 (-0.48, 0.44) micrograms/dL in the EFV group.

In the RPV group, 43/588 (7%) of participants with a normal 250 micrograms ACTH stimulation test at baseline developed an abnormal 250 micrograms ACTH stimulation test (peak cortisol level <18.1 micrograms/dL) during the trial compared to 18/561 (3%) in the EFV group. Of the participants who developed an abnormal 250 micrograms ACTH stimulation test during the trial, 14 participants in the RPV group and 9 participants in the EFV group had an abnormal 250 micrograms ACTH stimulation test at Week 96. Overall, there were no serious adverse events, deaths, or treatment discontinuations that could clearly be attributed to adrenal insufficiency. The clinical significance of the higher abnormal rate of 250 micrograms ACTH stimulation tests in the RPV group is not known.

Adverse Reactions in Clinical Trials of FTC+TAF with EVG+COBI in Treatment-Naïve Adult Participants with HIV-1

In pooled 48-week trials of antiretroviral treatment-naïve adult participants with HIV-1, the most common adverse reaction in participants treated with FTC+TAF with EVG+COBI (N=866) (incidence greater than or equal to 10%, all grades) was nausea (10%). In this treatment group, 0.9% of participants discontinued FTC+TAF with EVG+COBI due to adverse event [see Clinical Studies (14)]. Antiretroviral treatment-naïve adult participants treated with FTC+TAF with EVG+COBI experienced mean increases of 30 mg/dL of total cholesterol, 15 mg/dL of LDL cholesterol, 7 mg/dL of HDL cholesterol and 29 mg/dL of triglycerides after 48 weeks of use.

Renal Laboratory Tests

In two 48-week trials in antiretroviral treatment-naïve adults with HIV-1 treated with FTC+TAF with elvitegravir (EVG) plus cobicistat (COBI) (N=866) with a median baseline eGFR of 115 mL per minute, mean serum creatinine increased by 0.1 mg per dL from baseline to Week 48.

In clinical trials of FTC+TAF with EVG+COBI in treatment-naïve participants and in virologically-suppressed participants switched to FTC+TAF with EVG+COBI with estimated creatinine clearance greater than 50 mL per minute, renal serious adverse events or discontinuations due to renal adverse reactions were encountered in less than 1% of participants treated with FTC+TAF with EVG+COBI.

In a 24-week trial in adults with renal impairment (baseline eGFR 30 to 69 mL per minute) who received FTC+TAF with EVG+COBI (N=248), mean serum creatinine was 1.5 mg per dL at both baseline and Week 24. FTC+TAF with EVG+COBI was permanently discontinued due to worsening renal function in two of 80 (3%) participants.

Bone Mineral Density Effects

In the pooled analysis of two 48-week trials of antiretroviral treatment-naïve adult participants with HIV-1, bone mineral density (BMD) from baseline to Week 48 was assessed by dual-energy X-ray absorptiometry (DXA). Mean BMD decreased from baseline to Week 48 by -1.30% with FTC+TAF with EVG+COBI at the lumbar spine and -0.66% at the total hip. BMD declines of 5% or greater at the lumbar spine were experienced by 10% of FTC+TAF with EVG+COBI participants. BMD declines of 7% or greater at the femoral neck were experienced by 7% of FTC+TAF with EVG+COBI participants. The long-term clinical significance of these BMD changes is not known.

Adverse Reactions in Clinical Trials in Pediatric Participants with HIV-1

In an open-label 48-week trial (TMC278-C213 Cohort 1) of 36 antiretroviral treatment-naïve pediatric participants with HIV-1 aged 12 to less than 18 years (weighing at least 32 kg) treated with 25 mg per day of RPV and other antiretrovirals, the most common adverse reactions were headache (19%), depression (19%), somnolence (14%), nausea (11%), dizziness (8%), abdominal pain (8%), vomiting (6%) and rash (6%).

In an open-label 48-week trial (TMC278-C213 Cohort 2) of 18 antiretroviral treatment-naïve pediatric participants with HIV-1 aged 6 to less than 12 years (weighing at least 17 kg) treated with RPV and other antiretrovirals, the most common adverse reactions were decreased appetite (17%), vomiting (11%), ALT increased (11%), AST increased (11%), and rash (11%).

In an open-label 48-week trial (TMC278HTX2002) of 26 virologically suppressed participants with HIV-1 less than 12 years of age (weighing at least 16 kg) treated with RPV and other antiretrovirals, the most commen adverse reactions were vomiting (15%), abdominal pain (12%), nausea (8%), ALT increased (12%), AST increased (8%), and decreased appetite (8%).

In a 48-week, open-label trial, 50 antiretroviral treatment-naïve pediatric participants with HIV-1 aged 12 to less than 18 years and weighing at least 35 kg (Cohort 1) and 52 virologically-suppressed pediatric participants aged 6 to less than 12 years and weighing at least 25 kg (Cohort 2) received FTC+TAF with EVG+COBI. With the exception of a decrease in the mean CD4+ cell count observed in Cohort 2 of this study, the safety profile in pediatric participants who received this combination was similar to that in adults.

Bone Mineral Density Effects

Among the pediatric participants in Cohort 1 receiving FTC+TAF with EVG+COBI, mean BMD increased from baseline to Week 48, +4.2% at the lumbar spine and +1.3% for the total body less head (TBLH). Mean changes from baseline BMD Z-scores were -0.07 for lumbar spine and -0.20 for TBLH at Week 48. In cohort 1, one participant had significant (at least 4%) lumbar spine BMD loss at Week 48.

Among the pediatric participants in Cohort 2 receiving FTC+TAF with EVG+COBI, mean BMD increased from baseline to Week 48, +3.9% at the lumbar spine and +4.2% for TBLH. Mean changes from baseline BMD Z-scores were -0.24 for lumbar spine and -0.19 for TBLH at Week 48. In Cohort 2, six participants had significant (at least 4%) lumbar spine BMD loss at Week 48; 2 participants also had at least 4% TBLH BMD loss at Week 48.

Change from Baseline in CD4+ Cell Counts

Although all participants in Cohort 2 receiving FTC+TAF with EVG+COBI had HIV-1 RNA < 50 copies/mL, there was a decrease from baseline in CD4+ cell count at Weeks 24 and 48. The mean baseline and mean change from baseline in CD4+ cell count and in CD4% from Week 2 to Week 48 are presented in Table 3. All participants maintained their CD4+ cell counts above 400 cells/mm^3 [see Use in Specific Populations (8.4) and Clinical Studies (14.3)].

Table 3 Mean Change in CD4+ Count and CD4 Percentage from Baseline to Week 48 in Virologically-Suppressed Pediatric Patients from 6 to <12 Years Who Switched to FTC+TAF with EVG+COBI
 |  | Mean Change from Baseline
 | Baseline | Week 2 | Week 4 | Week 12 | Week 24 | Week 32 | Week 48
CD4+ Cell Count (cells/mm^3) | 961 (275.5) [Mean (SD)] | -117 | -114 | -112 | -118 | -62 | -66
CD4% | 38 (6.4) | +0.3% | -0.1% | -0.8% | -0.8% | -1.0% | -0.6%

Adrenal Function in Clinical Trials of RPV in Pediatric Participants

In trial TMC278-C213 Cohort 1, at Week 48, the overall mean change from baseline in basal cortisol showed an increase of 1.59 (0.24, 2.93) micrograms/dL.

Six of 30 (20%) participants with a normal 250 micrograms ACTH stimulation test at baseline developed an abnormal 250 micrograms ACTH stimulation test (peak cortisol level <18.1 micrograms/dL) during the trial. Three of these participants had an abnormal 250 micrograms ACTH stimulation test at Week 48. Overall, there were no serious adverse events, deaths, or treatment discontinuations that could clearly be attributed to adrenal insufficiency. The clinical significance of the abnormal 250 micrograms ACTH stimulation tests is not known.

In trial TMC278-C213 Cohort 2, basal cortisol at baseline was normal (≥9 μg/dL) for 4/18 participants, low for 13/18 participants, and missing for 1/18 participants.

Among the 4 participants with normal basal cortisol at baseline, 3 participants had either normal basal cortisol levels (≥9 μg/dL) or normal cortisol levels 1 hour after ACTH stimulation (≥18.1 μg/dL) throughout the trial and/or at the last available visit (Week 24 and Week 72), and 1 participant had low basal cortisol at the last available assessment (Week 48) and no ACTH stimulation test was performed. Among the 13 participants with low basal cortisol pre-dose at baseline, 2 participants had low basal and ACTH stimulated cortisol values throughout the trial, including ACTH stimulated cortisol at baseline before starting treatment with RPV. For both participants, no adverse events suggestive for adrenal insufficiency were reported. The remaining 11 participants had normal serum cortisol values after ACTH stimulation at baseline and/or during treatment.

In trial TMC278HTX2002, 15/26 participants had either normal basal cortisol (≥9 μg/dL) or normal cortisol 1 hour after ACTH stimulation (≥18.1 μg/dL), 9 had low basal cortisol on Day 1, and in 2 participants the baseline value was missing.

From the 19 participants with low basal cortisol at Week 48, in 15 participants, the Week 48 serum cortisol levels returned to normal (≥248 nmol/L) after repeat serum basal cortisol testing or was normal after ACTH stimulation testing (≥500 nmol/L). In 4 participants, the serum cortisol levels remained low after repeat serum basal cortisol testing or after ACTH stimulation testing. At Week 48, 6 participants had normal (basal) cortisol (≥9 ug/dL) and the Week 48 result was not available for 1 participant.

6.2 Postmarketing Experience

The following adverse reactions have been identified during postmarketing experience in patients receiving RPV or TAF-containing regimens. Because these reactions are reported voluntarily from a population of uncertain size, it is not always possible to reliably estimate their frequency or establish a causal relationship to drug exposure.

Rilpivirine:

Metabolism and Nutrition Disorders

Weight increased

Skin and Subcutaneous Tissue Disorders

Severe skin and hypersensitivity reactions including DRESS (Drug Reaction with Eosinophilia and Systemic Symptoms)

Renal and Urinary Disorders

Nephrotic syndrome

Tenofovir alafenamide:

Skin and Subcutaneous Tissue Disorders

Angioedema, urticaria, and rash

Renal and Urinary Disorders

Acute renal failure, acute tubular necrosis, proximal renal tubulopathy, and Fanconi syndrome

7 DRUG INTERACTIONS

7.1 Not Recommended with Other Antiretroviral Medications

Because ODEFSEY is a complete regimen, coadministration with other antiretroviral medications for the treatment of HIV-1 infection is not recommended.

7.2 Drugs Inducing or Inhibiting CYP3A Enzymes

RPV is primarily metabolized by CYP3A, and drugs that induce or inhibit CYP3A may affect the clearance of RPV [see Clinical Pharmacology (12.3)]. Coadministration of RPV and drugs that induce CYP3A may result in decreased plasma concentrations of RPV and loss of virologic response and possible resistance to RPV or to the class of NNRTIs [see Contraindications (4), Warnings and Precautions (5.6), and Table 4].

Coadministration of RPV and drugs that inhibit CYP3A may result in increased plasma concentrations of RPV and possible adverse events.

7.3 Drugs Inducing or Inhibiting P-glycoprotein

TAF, a component of ODEFSEY, is a substrate of P-gp, BCRP, OATP1B1, and OATP1B3. Drugs that strongly affect P-gp and BCRP activity may lead to changes in TAF absorption (see Table 4). Drugs that induce P-gp activity are expected to decrease the absorption of TAF, resulting in decreased plasma concentration of TAF, which may lead to loss of therapeutic effect of ODEFSEY and development of resistance. Coadministration of ODEFSEY with other drugs that inhibit P-gp and BCRP may increase the absorption and plasma concentration of TAF.

7.4 Drugs Increasing Gastric pH

Coadministration of RPV with drugs that increase gastric pH may decrease plasma concentrations of RPV and lead to loss of virologic response and possible resistance to RPV or to the class of NNRTIs. Use of RPV with proton pump inhibitors is contraindicated and use of RPV with H2-receptor antagonists requires staggered administration [see Contraindications (4) and Table 4].

7.5 QT Prolonging Drugs

There is limited information available on the potential for a pharmacodynamic interaction between RPV and drugs that prolong the QTc interval. In a study of healthy participants, higher than recommended doses of RPV, 75 mg once daily and 300 mg once daily (3 times and 12 times recommended daily dose in ODEFSEY) prolonged the QTc interval [see Warnings and Precautions (5.6) and Clinical Pharmacology (12.2)]. Consider alternative medications to ODEFSEY in patients taking a drug with a known risk of Torsade de Pointes.

7.6 Drugs Affecting Renal Function

Because FTC and tenofovir are primarily excreted by the kidneys by a combination of glomerular filtration and active tubular secretion, coadministration of ODEFSEY with drugs that reduce renal function or compete for active tubular secretion may increase concentrations of FTC, tenofovir, and other renally eliminated drugs and this may increase the risk of adverse reactions. Some examples of drugs that are eliminated by active tubular secretion include, but are not limited to, acyclovir, cidofovir, ganciclovir, valacyclovir, valganciclovir, aminoglycosides (e.g., gentamicin), and high-dose or multiple NSAIDs [see Warnings and Precautions (5.5)].

7.7 Significant Drug Interactions

Table 4 provides a listing of established or potentially clinically significant drug interactions with recommended steps to prevent or manage the drug interaction (the table is not all inclusive). The drug interactions described are based on studies conducted with either ODEFSEY, the components of ODEFSEY (FTC, RPV and TAF) as individual agents, or are predicted drug interactions that may occur with ODEFSEY [see Clinical Pharmacology (12.3), Tables 9–12]. For list of contraindicated drugs, [see Contraindications (4)].

Table 4 Significant [This table is not all inclusive.] Drug Interactions
Concomitant Drug Class: Drug Name | Effect on Concentration [Increase=↑; Decrease=↓; No Effect=↔] | Clinical Comment
Antacids: antacids (e.g., aluminum, magnesium hydroxide, or calcium carbonate) | ↔ RPV (antacids taken at least 2 hours before or at least 4 hours after RPV) ↓ RPV (concomitant intake) | Administer antacids at least 2 hours before or at least 4 hours after ODEFSEY.
Anticonvulsants: carbamazepine oxcarbazepine phenobarbital phenytoin | ↓ RPV | Coadministration is contraindicated due to potential for loss of virologic response and development of resistance.
Antimycobacterials: rifampin rifapentine | ↓ RPV | Coadministration is contraindicated due to potential for loss of virologic response and development of resistance.
Antimycobacterials: rifabutin | ↓ RPV [The interaction was evaluated in a clinical study. All other drug interactions shown are predicted.] ↓ TAF | Coadministration of ODEFSEY with rifabutin is not recommended.
Azole Antifungal Agents: fluconazole itraconazole ketoconazole posaconazole voriconazole | ↑ RPV, [This interaction study has been performed with a dose higher than the recommended dose for RPV. The dosing recommendation is applicable to the recommended dose of RPV 25 mg once daily.] ↑ TAF ↓ ketoconazole, | No dosage adjustment is required when ODEFSEY is coadministered with azole antifungal agents. Clinically monitor for breakthrough fungal infections when azole antifungals are coadministered with ODEFSEY.
Glucocorticoid (systemic): dexamethasone (more than a single dose) | ↓ RPV | Coadministration is contraindicated due to potential for loss of virologic response and development of resistance.
H2-Receptor Antagonists: cimetidine famotidine nizatidine ranitidine | ↔ RPV, (famotidine taken 12 hours before RPV or 4 hours after RPV) ↓ RPV, (famotidine taken 2 hours before RPV) | Administer H2-receptor antagonists at least 12 hours before or at least 4 hours after ODEFSEY.
Herbal Products: St. John's wort (Hypericum perforatum) | ↓ RPV | Coadministration is contraindicated due to potential for loss of virologic response and development of resistance.
Macrolide or Ketolide Antibiotics: clarithromycin erythromycin telithromycin | ↑ RPV ↔ clarithromycin ↔ erythromycin ↔ telithromycin | Where possible, alternatives such as azithromycin should be considered.
Narcotic Analgesics: methadone | ↓ R(–) methadone ↓ S(+) methadone ↔ RPV ↔ methadone (when used with tenofovir) | No dosage adjustments are required when initiating coadministration of methadone with ODEFSEY. However, clinical monitoring is recommended, as methadone maintenance therapy may need to be adjusted in some patients.
Proton Pump Inhibitors: e.g., dexlansoprazole, esomeprazole, lansoprazole, omeprazole, pantoprazole, rabeprazole | ↓ RPV | Coadministration is contraindicated due to potential for loss of virologic response and development of resistance.

7.8 Drugs Without Clinically Significant Interactions with ODEFSEY

Based on drug interaction studies conducted with the fixed dose combination or components of ODEFSEY, no clinically significant drug interactions have been observed when ODEFSEY is combined with the following drugs: acetaminophen, atorvastatin, chlorzoxazone, digoxin, ethinyl estradiol, ledipasvir, metformin, midazolam, norethindrone, norgestimate, sildenafil, simeprevir, sofosbuvir, velpatasvir, and voxilaprevir.

8 USE IN SPECIFIC POPULATIONS

8.1 Pregnancy

Pregnancy Exposure Registry

There is a pregnancy exposure registry that monitors pregnancy outcomes in individuals exposed to ODEFSEY during pregnancy. Healthcare providers are encouraged to register patients by calling the Antiretroviral Pregnancy Registry (APR) at 1-800-258-4263.

Risk Summary

Available data from the APR show no statistically significant difference in the overall risk of major birth defects for emtricitabine (FTC), rilpivirine (RPV) or tenofovir alafenamide (TAF) compared with the background rate for major birth defects of 2.7% in a US reference population of the Metropolitan Atlanta Congenital Defects Program (MACDP) (see Data). The rate of miscarriage is not reported in the APR. The estimated background rate of miscarriage in the clinically recognized pregnancies in the U.S. general population is 15–20%.

Based on the experience of pregnant individuals with HIV-1 who completed a clinical trial through the postpartum period with an RPV-based regimen, no dose adjustments are required for pregnant patients who are already on a stable RPV-containing regimen prior to pregnancy and who are virologically suppressed (HIV-1 RNA less than 50 copies per mL). Lower exposures of RPV were observed during pregnancy compared to the postpartum period. Therefore, viral load should be monitored closely [see Data and Clinical Pharmacology (12.3)].

In animal studies, no adverse developmental effects were observed when the components of ODEFSEY were administered separately during the period of organogenesis at exposures up to 60 and 108 times (mice and rabbits, respectively; FTC), 15 and 70 times (rats and rabbits, respectively; RPV) and equal to and 53 times (rats and rabbits, respectively; TAF) the exposure at the recommended daily dose of these components in ODEFSEY (see Data). Likewise, no adverse developmental effects were seen when FTC was administered to mice and RPV was administered to rats through lactation at exposures up to approximately 60 and 63 times, respectively, the exposure at the recommended daily dose of these components in ODEFSEY. No adverse effects were observed in the offspring when TDF was administered through lactation at tenofovir exposures of approximately 14 times the exposure at the recommended daily dosage of ODEFSEY.

Data

Human Data

Prospective reports from the APR of overall major birth defects in pregnancies exposed to drug components of ODEFSEY are compared with a U.S. background major birth defect rate. Methodological limitations of the APR include the use of MACDP as the external comparator group. The MACDP population is not disease-specific, evaluates women and infants from a limited geographic area, and does not include outcomes for births that occurred at less than 20 weeks gestation.

Emtricitabine (FTC):

Based on prospective reports to the APR of over 5,400 exposures to FTC-containing regimens during pregnancy resulting in live births (including over 3,900 exposed in the first trimester and over 1,500 exposed in the second/third trimester), the prevalence of birth defects in live births was 2.6% (95% CI: 2.2% to 3.2%) and 2.7% (95% CI: 1.9% to 3.7%) following first and second/third trimester exposure, respectively, to FTC-containing regimens.

Rilpivirine (RPV):

RPV in combination with a background regimen was evaluated in a clinical trial of 19 pregnant participants with HIV-1 during the second and third trimesters and postpartum. Each of the subjects were on an RPV-based regimen at the time of enrollment. Twelve participants completed the trial through the postpartum period (6–12 weeks after delivery) and pregnancy outcomes are missing for six participants. The exposure (C0h and AUC) of total RPV was approximately 30 to 40% lower during pregnancy compared with postpartum (6 to 12 weeks). The protein binding of RPV was similar (>99%) during second trimester, third trimester, and postpartum period [see Clinical Pharmacology (12.3)]. One participant discontinued the trial following fetal death at 25 weeks gestation due to suspected premature rupture of membranes. Among the 12 participants who were virologically suppressed at baseline (less than 50 copies/mL), virologic response was preserved in 10 participants (83.3%) through the third trimester visit and in 9 participants (75%) through the 6–12 week postpartum visit. Virologic outcomes during the third trimester visit were missing for two participants who were withdrawn (one participant was nonadherent to the study drug and one participant withdrew consent). Among the 10 infants with HIV test results available, born to 10 pregnant participants with HIV-1, all had test results that were negative for HIV-1 at the time of delivery and up to 16 weeks postpartum. All 10 infants received antiretroviral prophylactic treatment with zidovudine. RPV was well tolerated during pregnancy and postpartum. There were no new safety findings compared with the known safety profile of RPV in adults with HIV-1.

Based on prospective reports to the APR of over 750 exposures to RPV-containing regimens during pregnancy resulting in live births (including over 550 exposed in the first trimester and over 200 exposed in the second/third trimester), the prevalence of birth defects in live births was 1.4% (95% CI: 0.6% to 2.8%) and 1.5% (95% CI: 0.3% to 4.3%) following first and second/third trimester exposure, respectively, to RPV-containing regimens.

Tenofovir Alafenamide (TAF):

Based on prospective reports to the APR of over 660 exposures to TAF-containing regimens during pregnancy resulting in live births (including over 520 exposed in the first trimester and over 130 exposed in the second/third trimester), the prevalence of birth defects in live births was 4.2% (95% CI: 2.6% to 6.3%) and 3.0% (95% CI: 0.8% to 7.5%) following first and second/third trimester exposure, respectively, to TAF-containing regimens.

Animal Data

Emtricitabine: FTC was administered orally to pregnant mice (250, 500, or 1000 mg/kg/day) and rabbits (100, 300, or 1000 mg/kg/day) through organogenesis (on gestation days 6 through 15, and 7 through 19, respectively). No significant toxicological effects were observed in embryo-fetal toxicity studies performed with FTC in mice at exposures (AUC) approximately 60 times higher and in rabbits at approximately 108 times higher than human exposures at the recommended daily dose. In a pre/postnatal development study with FTC, mice were administered doses up to 1000 mg/kg/day; no significant adverse effects directly related to drug were observed in the offspring exposed daily from before birth (in utero) through sexual maturity at daily exposures (AUC) of approximately 60-fold higher than human exposures at the recommended daily dose.

Rilpivirine: RPV was administered orally to pregnant rats (40, 120, or 400 mg/kg/day) and rabbits (5, 10, or 20 mg/kg/day) through organogenesis (on gestation days 6 through 17, and 6 through 19, respectively). No significant toxicological effects were observed in embryo-fetal toxicity studies performed with RPV in rats and rabbits at exposures 15 (rats) and 70 (rabbits) times higher than the exposure in humans at the recommended dose of 25 mg once daily. In a pre/postnatal development study with RPV, where rats were administered up to 400 mg/kg/day through lactation, no significant adverse effects directly related to drug were noted in the offspring.

Tenofovir Alafenamide: TAF was administered orally to pregnant rats (25, 100, or 250 mg/kg/day) and rabbits (10, 30, or 100 mg/kg/day) through organogenesis (on gestation days 6 through 17, and 7 through 20, respectively). No adverse embryo-fetal effects were observed in rats and rabbits at TAF exposures similar to (rats) and approximately 53 (rabbits) times higher than the exposure in humans at the recommended daily dose of ODEFSEY. TAF is rapidly converted to tenofovir; the observed tenofovir exposure in rats and rabbits were 59 (rats) and 93 (rabbits) times higher than human tenofovir exposures at the recommended daily doses. Since TAF is rapidly converted to tenofovir and a lower tenofovir exposure in rats and mice was observed after TAF administration compared to tenofovir disoproxil fumarate (TDF, another prodrug for tenofovir) administration, a pre/postnatal development study in rats was conducted only with TDF. Doses up to 600 mg/kg/day were administered through lactation, no adverse effects were observed in the offspring on gestation day 7 [and lactation day 20] at tenofovir exposures of approximately 14 [21] times higher than the exposures in humans at the recommended daily dose of ODEFSEY.

8.2 Lactation

Risk Summary

Data from the published literature report the presence of FTC, TAF, and TFV (tenofovir) in human milk; it is unknown if RPV is present in human milk. RPV is present in rat milk (see Data). Data from the published literature have not reported adverse effects of FTC or TAF on a breastfed child; it is not known if RPV has effects on the breastfed child. It is not known if the components of ODEFSEY affect milk production.

Potential risks of breastfeeding include: (1) HIV-1 transmission to infants without HIV-1, (2) developing viral resistance in infants with HIV-1, and (3) adverse reactions in a breastfed infant similar to those seen in adults.

Data

Rilpivirine: In animals, no studies have been conducted to assess the excretion of RPV directly; however, RPV was measured in rat pups which were exposed through the milk of treated dams (dosed up to 400 mg/kg/day).

8.4 Pediatric Use

The efficacy and safety of ODEFSEY as a complete regimen for the treatment of HIV-1 was established in pediatric patients 6 years of age and older with body weight greater than or equal to 25 kg [see Dosage and Administration (2.2)]. No pediatric clinical trials were conducted with ODEFSEY. Use of ODEFSEY in this age group is supported by adequate and well-controlled studies of RPV+FTC+TDF in adults with HIV-1 infection, adequate and well-controlled studies of FTC+TAF with EVG+COBI in adults with HIV-1, and by the following pediatric studies conducted using the components of ODEFSEY [see Clinical Studies (14)]:

- 48-week open-label trials of antiretroviral treatment-naïve pediatric participants with HIV-1 aged 12 to less than 18 years and weighing at least 32 kg (N=36) and aged 6 to less than 12 years weighing at least 17 kg (N=18) treated with RPV and other antiretrovirals. The safety and efficacy of RPV administered with other antiretrovirals were similar to that in antiretroviral treatment-naïve adults with HIV-1 on this regimen [see Adverse Reactions (6.1) and Clinical Studies (14)].
- 48-week open-label trial of 26 virologically-suppressed pediatric participants with HIV-1 aged less than 12 years old and weighing at least 16 kg (N=26) treated with RPV and other antiretrovirals. The safety and efficacy of RPV administered with other antiretrovirals were similar to that in virologically-suppressed adults with HIV-1 on this regimen [see Adverse Reactions (6.1)]
- 48-week open-label trials of antiretroviral treatment-naïve pediatric participants with HIV-1 aged 12 to less than 18 years and weighing at least 35 kg (N=50) and virologically-suppressed pediatric participants between the ages of 6 to less than 12 years weighing at least 25 kg (N=52) treated with FTC+TAF with EVG+COBI. The safety and efficacy of FTC+TAF with EVG+COBI were similar to that in adults with HIV-1 on this regimen, with the exception of a decrease from baseline in CD4+ cell counts in participants 6 to less than 12 years of age weighing at least 25 kg [see Adverse Reactions (6.1) and Clinical Studies (14)].

Because it is a fixed-dose combination tablet, the dose of ODEFSEY cannot be adjusted for patients of lower age and weight. The safety and efficacy of ODEFSEY have not been established in pediatric patients weighing less than 25 kg [see Clinical Pharmacology (12.3) and Clinical Studies (14)].

8.5 Geriatric Use

In clinical trials, 80 of the 97 participants enrolled aged 65 years and over received FTC+TAF with EVG+COBI. No differences in safety or efficacy have been observed between elderly participants and those between 12 and less than 65 years of age. Clinical trials of RPV did not include sufficient numbers of participants aged 65 years and over to determine whether they respond differently from younger participants [see Clinical Pharmacology (12.3)].

8.6 Renal Impairment

No dosage adjustment of ODEFSEY is recommended in patients with estimated creatinine clearance greater than or equal to 30 mL per minute. ODEFSEY should be used with caution in adults patients with ESRD (estimated creatinine clearance below 15mL per minute) who are receiving chronic hemodialysis and increased monitoring is recommended for RPV-related adverse effects in patients with ESRD, as RPV concentrations may be increased due to alteration of drug absorption, distribution, and metabolism secondary to renal dysfunction. On days of hemodialysis, administer the daily dose of ODEFSEY after completion of hemodialysis treatment [see Dosage and Administration (2.4) and Clinical Pharmacology (12.3)].

ODEFSEY is not recommended in patients with severe renal impairment (estimated creatinine clearance of 15 to below 30 mL per minute), or in patients with ESRD who are not receiving chronic hemodialysis, as the safety of ODEFSEY has not been established in these populations [see Dosage and Administration (2.4) and Clinical Pharmacology (12.3)].

8.7 Hepatic Impairment

No dosage adjustment of ODEFSEY is recommended in patients with mild (Child-Pugh Class A) or moderate (Child-Pugh Class B) hepatic impairment. ODEFSEY has not been studied in patients with severe hepatic impairment (Child-Pugh Class C) [see Clinical Pharmacology (12.3)].

10 OVERDOSAGE

Limited data are available on overdose of the components of ODEFSEY in patients. If overdose occurs, monitor the patient for evidence of toxicity. Treatment of overdose with ODEFSEY consists of general supportive measures including monitoring of vital signs and ECG (QT interval) as well as observation of the clinical status of the patient.

Emtricitabine (FTC): Hemodialysis treatment removes approximately 30% of the FTC dose over a 3-hour dialysis period starting within 1.5 hours of FTC dosing (blood flow rate of 400 mL per minute and a dialysate flow rate of 600 mL per minute). It is not known whether FTC can be removed by peritoneal dialysis.

Rilpivirine (RPV): Human experience of overdose with RPV is limited. There is no specific antidote for overdose with RPV. Since RPV is highly bound to plasma protein, dialysis is unlikely to result in significant removal of RPV.

Tenofovir Alafenamide (TAF): Tenofovir is efficiently removed by hemodialysis with an extraction coefficient of approximately 54%.

11 DESCRIPTION

ODEFSEY (emtricitabine, rilpivirine, and tenofovir alafenamide) is a fixed-dose combination tablet containing emtricitabine (FTC), rilpivirine (RPV), and tenofovir alafenamide (TAF) for oral administration.

- FTC, a synthetic nucleoside analog of cytidine, is an HIV-1 nucleoside analog reverse transcriptase inhibitor (HIV-1 NRTI).
- RPV is an HIV-1 non-nucleoside reverse transcriptase inhibitor (NNRTI).
- TAF, an HIV-1 NRTI, is converted in vivo to tenofovir, an acyclic nucleoside phosphonate (nucleotide) analog of adenosine 5′-monophosphate.

Each tablet contains 200 mg of FTC, 25 mg of RPV (equivalent to 27.5 of rilpivirine hydrochloride) and 25 mg of TAF (equivalent to 28 mg of tenofovir alafenamide fumarate) and the following inactive ingredients: croscarmellose sodium, lactose monohydrate, magnesium stearate, microcrystalline cellulose, polysorbate 20, and povidone. The tablets are film-coated with a coating material containing iron oxide black, polyethylene glycol, polyvinyl alcohol, talc, and titanium dioxide.

Emtricitabine: The chemical name of FTC is 4-amino-5-fluoro-1-(2R-hydroxymethyl-1,3-oxathiolan-5S-yl)-(1H)-pyrimidin-2-one. FTC is the (-)enantiomer of a thio analog of cytidine, which differs from other cytidine analogs in that it has a fluorine in the 5 position.

FTC has a molecular formula of C8H10FN3O3S and a molecular weight of 247.24 and has the following structural formula:

FTC is a white to off-white powder with a solubility of approximately 112 mg per mL in water at 25 °C.

Rilpivirine: The chemical name of rilpivirine hydrochloride drug substance is 4-[[4-[[4-[(E)-2-cyanoethenyl]-2,6-dimethylphenyl]amino]-2-pyrimidinyl]amino]benzonitrile monohydrochloride. Its molecular formula is C22H18N6 ∙ HCl and its molecular weight is 402.88. Rilpivirine hydrochloride has the following structural formula:

Rilpivirine hydrochloride is a white to almost white powder. Rilpivirine hydrochloride is practically insoluble in water over a wide pH range.

Tenofovir Alafenamide: The chemical name of tenofovir alafenamide fumarate drug substance is L-alanine, N-[(S)-[[(1R)-2-(6-amino-9H-purin-9-yl)-1-methylethoxy]methyl]phenoxyphosphinyl]-, 1-methylethyl ester, (2E)-2-butenedioate (2:1).

Tenofovir alafenamide fumarate has an empirical formula of C21H29O5N6P∙½(C4H4O4) and a formula weight of 534.50 and has the following structural formula:

Tenofovir alafenamide fumarate is a white to off-white or tan powder with a solubility of 4.7 mg per mL in water at 20 °C.

12 CLINICAL PHARMACOLOGY

12.1 Mechanism of Action

ODEFSEY is a fixed dose combination of antiretroviral drugs emtricitabine, rilpivirine, and tenofovir alafenamide [see Microbiology (12.4)].

12.2 Pharmacodynamics

Cardiac Electrophysiology

When higher than recommended RPV doses of 75 mg (3 times the recommended dosage in ODEFSEY) once daily and 300 mg (12 times the recommended dosage in ODEFSEY) once daily were studied in healthy adults, the maximum mean time-matched (95% upper confidence bound) differences in QTcF interval from placebo after baseline correction were 10.7 (15.3) and 23.3 (28.4) milliseconds, respectively. Steady-state administration of RPV 75 mg once daily and 300 mg once daily resulted in a mean steady-state Cmax approximately 2.6 times and 6.7 times, respectively, higher than the mean Cmax observed with the recommended 25 mg once daily dose of RPV [see Warnings and Precautions (5.6)].

The effect of RPV at the recommended dose of 25 mg once daily on the QTcF interval was evaluated in a randomized, placebo-, and active- (moxifloxacin 400 mg once daily) controlled crossover study in 60 healthy adults, with 13 measurements over 24 hours at steady state. The maximum mean time-matched (95% upper confidence bound) differences in QTcF interval from placebo after baseline correction was 2 (5) milliseconds (i.e., below the threshold of clinical concern).

In a thorough QT/QTc study in 48 healthy participants, TAF at the recommended dose and at a dose approximately 5 times the recommended dose, did not affect the QT/QTc interval and did not prolong the PR interval.

The effect of FTC on the QT interval is not known.

12.3 Pharmacokinetics

Absorption, Distribution, Metabolism, and Excretion

The pharmacokinetic properties of the components of ODEFSEY are provided in Table 5. The multiple dose pharmacokinetic parameters of FTC, RPV and TAF and its metabolite tenofovir are provided in Table 6.

Table 5 Pharmacokinetic Properties of the Components of ODEFSEY
 | Rilpivirine | Emtricitabine | Tenofovir Alafenamide
Absorption
Tmax (h) | 4 | 3 | 1
Effect of moderate fat meal (relative to fasting) [Values refer to geometric mean ratio [fed/ fasted] in PK parameters and (90% confidence interval). High-calorie/high-fat meal = ~800 kcal, 50% fat. Moderate-fat meal = ~600 kcal, 27% fat.] | AUC Ratio = 1.13 (1.03, 1.23) | AUC Ratio = 0.91 (0.89, 0.93) | AUC Ratio = 1.45 (1.33, 1.58)
Effect of high fat meal (relative to fasting) | AUC Ratio = 1.72 (1.49, 1.99) | AUC Ratio = 0.88 (0.85, 0.90) | AUC Ratio = 1.53 (1.39, 1.69)
Distribution
% Bound to human plasma proteins | ~99 | <4 | ~80
Source of protein binding data | In vitro | In vitro | Ex vivo
Blood-to-plasma ratio | 0.7 | 0.6 | 1.0
Metabolism
Metabolism | CYP3A | Not significantly metabolized | Cathepsin A [In vivo, TAF is hydrolyzed within cells to form tenofovir (major metabolite), which is phosphorylated to the active metabolite, tenofovir diphosphate. In vitro studies have shown that TAF is metabolized to tenofovir by cathepsin A in PBMCs and macrophages; and by CES1 in hepatocytes. Upon coadministration with the moderate CYP3A inducer probe efavirenz, TAF exposure was unaffected.] (PBMCs) CES1 (hepatocytes) CYP3A (minimal)
Elimination
Major route of elimination | Metabolism | Glomerular filtration and active tubular secretion | Metabolism (>80% of oral dose)
t1/2 (h) [t1/2 values refer to median terminal plasma half-life. Note that the pharmacologically active metabolite, tenofovir diphosphate, has a half-life of 150–180 hours within PBMCs.] | 50 | 10 | 0.51
% Of dose excreted in urine [Dosing in mass balance studies: FTC (single dose administration of [^14C] emtricitabine after multiple dosing of emtricitabine for ten days); TAF (single dose administration of [^14C] tenofovir alafenamide).] | 6 | 70 | <1
% Of dose excreted in feces | 85 | 13.7 | 31.7
PBMCs = peripheral blood mononuclear cells; CES1 = carboxylesterase 1.

Table 6 Multiple Dose Pharmacokinetic Parameters of Emtricitabine, Rilpivirine, Tenofovir Alafenamide and its Metabolite Tenofovir Following Oral Administration with a Meal in Adults with HIV-1
Parameter Mean (CV%) | Emtricitabine [From Intensive PK analysis in a phase 2 trial in adults with HIV-1 treated with FTC+TAF with EVG+COBI (n=19).] | Rilpivirine [From Population PK analysis in a trial of treatment-naïve adults with HIV-1 treated with RPV (n=679).] | Tenofovir Alafenamide [From Population PK analysis in two trials of treatment-naïve adults with HIV-1 treated within EVG+COBI+FTC+TAF (n=539).] | Tenofovir [From Population PK analysis in two trials of treatment-naïve adults with HIV-1 treated with EVG+COBI+FTC+TAF (n=841).]
Cmax (microgram per mL) | 2.1 (20.2) | NA | 0.16 (51.1) | 0.02 (26.1)
AUCtau (microgram∙hour per mL) | 11.7 (16.6) | 2.2 (38.1) | 0.21 (71.8) | 0.29 (27.4)
Ctrough (microgram per mL) | 0.10 (46.7) | 0.08 (44.3) | NA | 0.01 (28.5)
CV = Coefficient of Variation; NA = Not Applicable

Specific Populations

Geriatric Patients

The pharmacokinetics of FTC and TAF have not been fully evaluated in the elderly (65 years of age and older). Population pharmacokinetics analysis of participants with HIV-1 in Phase 2 and Phase 3 trials of FTC+TAF with EVG+COBI showed that age did not have a clinically relevant effect on exposures of TAF up to 75 years of age.

The pharmacokinetics of RPV have not been fully evaluated in the elderly (65 years of age and older) [see Use in Specific Populations (8.5)].

Pediatric Patients

Exposures of TAF in 24 pediatric participants with HIV-1 aged 12 to less than 18 years who received FTC+TAF with EVG+COBI were decreased (23% for TAF AUC) compared to exposures achieved in treatment-naïve adults following administration of FTC+TAF with EVG+COBI. These exposure differences are not thought to be clinically significant based on exposure-response relationships. FTC exposures were similar in adolescents compared to treatment-naïve adults.

Exposures of FTC, TAF and TFV in 23 pediatric participants with HIV-1 aged 6 to less than 12 years who received FTC+TAF with EVG+COBI were higher (50 to 80% for AUC) than exposures achieved in adults following the administration of FTC+TAF with EVG+COBI, however, the increase was not considered clinically significant as the safety profiles were similar in adult and pediatric participants.

The PK of RPV in pediatric participants with HIV aged 6 to less than 18 years who received RPV 25 mg once daily were comparable to or slightly higher than those obtained in adults with HIV-1 [see Use In Specific Populations (8.4)].

Race and Gender

No clinically significant changes in the pharmacokinetics of the components of ODEFSEY have been observed based on race or gender.

Patients with Renal Impairment

Rilpivirine: Population pharmacokinetic analysis indicated that RPV exposure was similar in participants with HIV-1 and eGFR 60 to 89 mL per minute by Cockcroft-Gault method, relative to participants with HIV-1 and normal renal function. There is limited or no information regarding the pharmacokinetics of RPV in patients with moderate or severe renal impairment or in patients with end-stage renal disease [see Use in Specific Populations (8.6)].

Emtricitabine and Tenofovir Alafenamide: The pharmacokinetics of FTC+TAF with EVG+COBI in participants with HIV-1 and renal impairment (eGFR 30 to 69 mL per minute by Cockcroft-Gault method), and in participants with HIV-1 and ESRD (estimated creatinine clearance of less than 15 mL per minute by Cockcroft-Gault method) receiving chronic hemodialysis were evaluated in subsets of virologically-suppressed participants in open-label trials. The pharmacokinetics of TAF were similar among healthy participants, participants with HIV-1 and mild or moderate renal impairment, and participants with HIV-1 and ESRD receiving chronic hemodialysis; increases in FTC and TFV exposures in participants with HIV-1 and renal impairment were not considered clinically relevant (Table 7).

Table 7 Pharmacokinetics of FTC and a Metabolite of TAF (Tenofovir) in Adults with HIV-1 and Renal Impairment as Compared to Participants with Normal Renal Function
 | AUCtau (microgram-hour per mL) Mean (CV%)
Estimated Creatinine Clearance [By Cockcroft-Gault method.] | ≥90 mL per minute (N=18) [From a phase 2 trial in adults with HIV-1 and normal renal function treated with FTC+TAF with EVG+COBI.] | 60–89 mL per minute (N=11) [These participants had an eGFR ranging from 60 to 69 mL per minute.] | 30–59 mL per minute (N=18) [From a phase 3 trial in adults with HIV-1 and renal impairment treated with FTC+TAF with EVG+COBI.] | <15 mL per minute (N=12) [From a phase 3 trial in adults with HIV-1 and ESRD receiving chronic hemodialysis treated with FTC+TAF with EVG+COBI; PK assessed prior to hemodialysis following 3 consecutive daily doses of FTC+TAF with EVG+COBI.]
Emtricitabine | 11.4 (11.9) | 17.6 (18.2) | 23.0 (23.6) | 62.9 (48.0) [N=11.]
Tenofovir | 0.32 (14.9) | 0.46 (31.5) | 0.61 (28.4) | 8.72 (39.4) [N=10.]

Patients with Hepatic Impairment

Emtricitabine: The pharmacokinetics of FTC have not been studied in participants with hepatic impairment; however, FTC is not significantly metabolized by liver enzymes, so the impact of hepatic impairment should be limited.

Rilpivirine: In a study comparing 8 participants with mild hepatic impairment (Child-Pugh score A) to 8 matched controls and 8 participants with moderate hepatic impairment (Child-Pugh score B) to 8 matched controls, the multiple-dose exposure of RPV was 47% higher in participants with mild hepatic impairment and 5% higher in participants with moderate hepatic impairment [see Use in Specific Populations (8.7)].

Tenofovir Alafenamide: Clinically relevant changes in the pharmacokinetics of tenofovir alafenamide or its metabolite tenofovir were not observed in participants with mild, moderate (Child-Pugh A and B), or severe hepatic impairment (Child-Pugh C) [see Use in Specific Populations (8.7)].

Hepatitis B and/or Hepatitis C Virus Coinfection

The pharmacokinetics of FTC and TAF have not been fully evaluated in participants with hepatitis B and/or C virus. Population pharmacokinetic analysis indicated that hepatitis B and/or C virus coinfection had no clinically relevant effect on the exposure of RPV.

Pregnancy and Postpartum

Rilpivirine: The exposure (C0h and AUC24h) to total RPV after intake of RPV 25 mg once daily as part of an antiretroviral regimen was 30 to 40% lower during pregnancy (similar for the second and third trimester), compared with postpartum (see Table 8). However, the exposure during pregnancy was not significantly different from exposures obtained in Phase 3 trials of RPV-containing regimens. Based on the exposure-response relationship for RPV, this decrease is not considered clinically relevant in patients who are virologically-suppressed. The protein binding of RPV was similar (>99%) during the second trimester, third trimester, and postpartum.

Table 8 Pharmacokinetic Results of Total Rilpivirine After Administration of Rilpivirine 25 mg Once Daily as Part of an Antiretroviral Regimen, During the 2nd Trimester of Pregnancy, the 3rd Trimester of Pregnancy and Postpartum
Pharmacokinetics of total rilpivirine (mean ± SD, tmax: median [range]) | Postpartum (6–12 Weeks) (n=11) | 2nd Trimester of pregnancy (n=15) | 3rd Trimester of pregnancy (n=13)
C0h, ng/mL | 111 ± 69.2 | 65.0 ± 23.9 | 63.5 ± 26.2
Cmin, ng/mL | 84.0 ± 58.8 | 54.3 ± 25.8 | 52.9 ± 24.4
Cmax, ng/mL | 167 ± 101 | 121 ± 45.9 | 123 ± 47.5
tmax, h | 4.00 (2.03–25.08) | 4.00 (1.00–9.00) | 4.00 (2.00–24.93)
AUC24h, ng.h/mL | 2714 ± 1535 | 1792 ± 711 | 1762 ± 662

Drug Interaction Studies

Rilpivirine: RPV is primarily metabolized by CYP3A, and drugs that induce or inhibit CYP3A may thus affect the clearance of RPV.

RPV at a dose of 25 mg once daily is not likely to have a clinically relevant effect on the exposure of medicinal products metabolized by CYP enzymes.

TAF is not an inhibitor of CYP1A2, CYP2B6, CYP2C8, CYP2C9, CYP2C19, CYP2D6, or UGT1A1. TAF is a weak inhibitor of CYP3A in vitro. TAF is not an inhibitor or inducer of CYP3A in vivo.

The drug interaction studies described in Tables 9–12 were conducted with ODEFSEY (FTC/RPV/TAF) or the components of ODEFSEY (FTC, RPV, or TAF) administered individually.

The effects of coadministered drugs on the exposures of RPV and TAF are shown in Tables 9 and 10, respectively. The effects of RPV and TAF on the exposure of coadministered drugs are shown in Tables 11 and 12, respectively. For information regarding clinical recommendations, see Drug Interactions (7).

Table 9 Changes in Pharmacokinetic Parameters for RPV in the Presence of Coadministered Drugs in Healthy Participants
Coadministered Drug | Dose/Schedule |  |  | Mean Ratio of RPV Pharmacokinetic Parameters With/Without Coadministered Drug (90% CI); No Effect = 1.00
Coadministered Drug | Coadministered Drug (mg) | RPV (mg) | N | Cmax | AUC | Cmin
Acetaminophen | 500 single dose | 150 once daily [25 mg, 75 mg, and 150 mg of RPV is 1, 3, and 6 times the recommended dose of RPV in ODEFSEY, respectively.] | 16 | 1.09 (1.01, 1.18) | 1.16 (1.10, 1.22) | 1.26 (1.16, 1.38)
Atorvastatin | 40 once daily | 150 once daily | 16 | 0.91 (0.79, 1.06) | 0.90 (0.81, 0.99) | 0.90 (0.84, 0.96)
Chlorzoxazone | 500 single dose taken 2 hours after RPV | 150 once daily | 16 | 1.17 (1.08, 1.27) | 1.25 (1.16, 1.35) | 1.18 (1.09, 1.28)
Ethinylestradiol/Norethindrone | 0.035 once daily /1 mg once daily | 25 once daily [Study conducted with RPV.] | 15 | ↔ [Comparison based on historic controls.] | ↔ | ↔
Famotidine | 40 single dose taken 12 hours before RPV | 150 single dose | 24 | 0.99 (0.84, 1.16) | 0.91 (0.78, 1.07) | NA
Famotidine | 40 single dose taken 2 hours before RPV | 150 single dose | 23 | 0.15 (0.12, 0.19) | 0.24 (0.20, 0.28) | NA
Famotidine | 40 single dose taken 4 hours after RPV | 150 single dose | 24 | 1.21 (1.06, 1.39) | 1.13 (1.01, 1.27) | NA
Ketoconazole | 400 once daily | 150 once daily | 15 | 1.30 (1.13, 1.48) | 1.49 (1.31, 1.70) | 1.76 (1.57, 1.97)
Methadone | 60–100 once daily, individualized dose | 25 once daily | 12 | ↔ | ↔ | ↔
Ledipasvir/Sofosbuvir | 90/400 once daily | 25 once daily [Study conducted with ODEFSEY (FTC/RPV/TAF).] | 42 | 0.97 (0.92, 1.02) | 0.95 (0.91, 0.98) | 0.93 (0.89, 0.97)
Omeprazole | 20 once daily | 25 single dose | 15 | 0.30 (0.24, 0.38) | 0.35 (0.28, 0.44) | NA
Rifabutin | 300 once daily | 25 once daily | 18 | 0.69 (0.62, 0.76) | 0.58 (0.52, 0.65) | 0.52 (0.46, 0.59)
Rifampin | 600 once daily | 150 once daily | 16 | 0.31 (0.27, 0.36) | 0.20 (0.18, 0.23) | 0.11 (0.10, 0.13)
Simeprevir | 25 once daily | 150 once daily | 23 | 1.04 (0.95, 1.30) | 1.12 (1.05, 1.19) | 1.25 (1.16, 1.35)
Sildenafil | 50 single dose | 75 once daily | 16 | 0.92 (0.85, 0.99) | 0.98 (0.92, 1.05) | 1.04 (0.98, 1.09)
Sofosbuvir/velpatasvir | 400/100 once daily | 10 once daily [Study conducted with FTC/RPV/TDF.] | 24 | 0.93 (0.88,0.98) | 0.95 (0.90, 1.00) | 0.96 (0.90,1.03)
Sofosbuvir/velpatasvir/voxilaprevir | 400/100/100 + 100 voxilaprevir [Study conducted with additional voxilaprevir 100 mg to achieve voxilaprevir exposures expected in HCV patients.] once daily | 25 once daily | 30 | 0.79 (0.74, 0.84) | 0.80 (0.76, 0.85) | 0.82 (0.77, 0.87)
CI=Confidence Interval; N=maximum number of participants with data; NA=Not Available; ↔=no change

Table 10 Changes in Pharmacokinetic Parameters for TAF in the Presence of the Coadministered Drug in Healthy Participants
Coadministered Drug | Dose of Coadministered Drug (mg) | TAF (mg) | N | Mean Ratio of Tenofovir Alafenamide Pharmacokinetic Parameters (90% CI); No Effect = 1.00
Coadministered Drug | Dose of Coadministered Drug (mg) | TAF (mg) | N | Cmax | AUC | Cmin
Cobicistat [Increases TAF exposure via inhibition of intestinal P-glycoprotein.] | 150 once daily | 8 once daily | 12 | 2.83 (2.20, 3.65) | 2.65 (2.29, 3.07) | NA
Ledipasvir/Sofosbuvir | 90/400 once daily | 25 once daily [Study conducted with ODEFSEY (FTC/RPV/TAF).] | 42 | 1.03 (0.94, 1.14) | 1.32 (1.25, 1.40) | NA
Sofosbuvir/velpatasvir/voxilaprevir | 400/100/100 + 100 voxilaprevir [Study conducted with additional voxilaprevir 100 mg to achieve voxilaprevir exposures expected in patients with HCV.] once daily | 25 once daily | 30 | 1.32 (1.17, 1.48) | 1.52 (1.43,1.61) | NA
CI=Confidence Interval; N=maximum number of participants with data; NA=Not Available

Table 11 Changes in Pharmacokinetic Parameters for Coadministered Drugs in the Presence of RPV in Healthy Participants
Coadministered Drug | Dose/Schedule |  |  | Mean Ratio of Coadministered Drug Pharmacokinetic Parameters With/Without RPV (90% CI); No Effect = 1.00
Coadministered Drug | Coadministered Drug (mg) | RPV (mg) | N | Cmax | AUC | Cmin
Acetaminophen | 500 single dose | 150 once daily [25 mg, 75 mg, and 150 mg of RPV is 1, 3, and 6 times the recommended dose of RPV in ODEFSEY, respectively.] | 16 | 0.97 (0.86, 1.10) | 0.92 (0.85, 0.99) | NA
Atorvastatin | 40 once daily | 150 once daily | 16 | 1.35 (1.08, 1.68) | 1.04 (0.97, 1.12) | 0.85 (0.69, 1.03)
2-hydroxy-atorvastatin | 40 once daily | 150 once daily | 16 | 1.58 (1.33, 1.87) | 1.39 (1.29, 1.50) | 1.32 (1.10, 1.58)
4-hydroxy-atorvastatin | 40 once daily | 150 once daily | 16 | 1.28 (1.15, 1.43) | 1.23 (1.13, 1.33) | NA
Chlorzoxazone | 500 single dose taken 2 hours after RPV | 150 once daily | 16 | 0.98 (0.85, 1.13) | 1.03 (0.95, 1.13) | NA
Digoxin | 0.5 single dose | 25 once daily [Study conducted with RPV.] | 22 | 1.06 (0.97, 1.17) | 0.98 (0.93, 1.04) [AUC(0–last).] | NA
Ethinylestradiol | 0.035 once daily | 25 once daily | 17 | 1.17 (1.06, 1.30) | 1.14 (1.10, 1.19) | 1.09 (1.03, 1.16)
Norethindrone | 1 mg once daily | 25 once daily | 17 | 0.94 (0.83, 1.06) | 0.89 (0.84, 0.94) | 0.99 (0.90, 1.08)
Ketoconazole | 400 once daily | 150 once daily | 14 | 0.85 (0.80, 0.90) | 0.76 (0.70, 0.82) | 0.34 (0.25, 0.46)
Ledipasvir | 90 once daily | 25 once daily [Study conducted with ODEFSEY (FTC/RPV/TAF).] | 41 | 1.01 (0.97, 1.05) | 1.02 (0.97, 1.06) | 1.02 (0.98, 1.07)
Sofosbuvir | 400 once daily | 25 once daily | 41 | 0.96 (0.89, 1.04) | 1.05 (1.01, 1.09) | NA
GS-331007 [The predominant circulating nucleoside metabolite of sofosbuvir.] | 400 once daily | 25 once daily | 41 | 1.08 (1.05, 1.11) | 1.08 (1.06, 1.10) | 1.10 (1.07, 1.12)
R(-) methadone | 60–100 once daily, individualized dose | 25 once daily | 13 | 0.86 (0.78, 0.95) | 0.84 (0.74, 0.95) | 0.78 (0.67, 0.91)
S(+) methadone | 60–100 once daily, individualized dose | 25 once daily | 13 | 0.87 (0.78, 0.97) | 0.84 (0.74, 0.96) | 0.79 (0.67, 0.92)
Metformin | 850 single dose | 25 once daily | 20 | 1.02 (0.95, 1.10) | 0.97 (0.90,1.06) [N (maximum number of participants with data for AUC(0–∞)=15)] | NA
Rifampin | 600 once daily | 150 once daily | 16 | 1.02 (0.93, 1.12) | 0.99 (0.92, 1.07) | NA
25-desacetylrifampin | 600 once daily | 150 once daily | 16 | 1.00 (0.87, 1.15) | 0.91 (0.77, 1.07) | NA
Simeprevir | 150 once daily | 25 once daily | 21 | 1.10 (0.97, 1.26) | 1.06 (0.94, 1.19) | 0.96 (0.83, 1.11)
Sildenafil | 50 single dose | 75 once daily | 16 | 0.93 (0.80, 1.08) | 0.97 (0.87, 1.08) | NA
N-desmethyl-sildenafil | 50 single dose | 75 once daily | 16 | 0.90 (0.80, 1.02) | 0.92 (0.85, 0.99) | NA
Sofosbuvir GS-331007 | 400 once daily | 25 once daily [Study conducted with FTC/RPV/TDF.] | 24 | 1.09 (0.95, 1.25) 0.96 (0.90, 1.01) | 1.16 (1.10, 1.24) 1.04 (1.00, 1.07) | NA 1.12 (1.07, 1.17)
Velpatasvir | 100 once daily | 25 once daily | 24 | 0.96 (0.85, 1.10) | 0.99 (0.88, 1.11) | 1.02 (0.91, 1.15)
Sofosbuvir | 400 once daily | 25 once daily | 30 | 0.95 (0.86, 1.05) | 1.01 (0.97, 1.06) | NA
GS-331007 | 400 once daily | 25 once daily | 30 | 1.02 (0.98, 1.06) | 1.04 (1.01, 1.06) | NA
Velpatasvir | 100 once daily | 25 once daily | 30 | 1.05 (0.96, 1.16) | 1.01 (0.94, 1.07) | 1.01 (0.95, 1.09)
Voxilaprevir | 100 + 100 once daily | 25 once daily | 30 | 0.96 (0.84, 1.11) | 0.94 (0.84, 1.05) | 1.02 (0.92, 1.12)
CI=Confidence Interval; N=maximum number of participants with data; NA=Not Available

Table 12 Changes in Pharmacokinetic Parameters for Coadministered Drug in the Presence of TAF in Healthy Participants
Coadministered Drug | Dose of Coadministered Drug (mg) | TAF (mg) | N | Mean Ratio of Coadministered Drug Pharmacokinetic Parameters (90% CI); No Effect = 1.00
Coadministered Drug | Dose of Coadministered Drug (mg) | TAF (mg) | N | Cmax | AUC | Cmin
Midazolam [A sensitive CYP3A4 substrate.] | 2.5 single dose, orally | 25 once daily [Study conducted with TAF.] | 18 | 1.02 (0.92, 1.13) | 1.13 (1.04, 1.23) | NA
Midazolam [A sensitive CYP3A4 substrate.] | 1 single dose, IV | 25 once daily [Study conducted with TAF.] | 18 | 0.99 (0.89, 1.11) | 1.08 (1.04, 1.13) | NA
Ledipasvir [Study conducted with ODEFSEY (FTC/RPV/TAF).] | 90/400 once daily | 25 once daily | 41 | 1.01 (0.97, 1.05) | 1.02 (0.97, 1.06) | 1.02 (0.98,1.07)
Sofosbuvir | 90/400 once daily | 25 once daily | 41 | 0.96 (0.89, 1.04) | 1.05 (1.01, 1.09) | NA
GS-331007, [The predominant circulating nucleoside metabolite of sofosbuvir.] | 90/400 once daily | 25 once daily | 41 | 1.08 (1.05, 1.11) | 1.08 (1.06, 1.10) | 1.10 (1.07, 1.12)
Norelgestromin | norgestimate 0.180/0.215/0.250 once daily/ethinyl estradiol 0.025 once daily | 25 once daily [Study conducted with FTC/TAF.] | 29 | 1.17 (1.07,1.26) | 1.12 (1.07, 1.17) | 1.16 (1.08,1.24)
Norgestrel | norgestimate 0.180/0.215/0.250 once daily/ethinyl estradiol 0.025 once daily | 25 once daily [Study conducted with FTC/TAF.] | 29 | 1.10 (1.02, 1.18) | 1.09 (1.01, 1.18) | 1.11 (1.03,1.20)
Ethinyl estradiol | norgestimate 0.180/0.215/0.250 once daily/ethinyl estradiol 0.025 once daily | 25 once daily [Study conducted with FTC/TAF.] | 29 | 1.22 (1.15, 1.29) | 1.11 (1.07, 1.16) | 1.02 (0.93,1.12)
Sofosbuvir | 400 once daily | 25 once daily | 30 | 0.95 (0.86, 1.05) | 1.01 (0.97, 1.06) | NA
GS-331007 | 400 once daily | 25 once daily | 30 | 1.02 (0.98, 1.06) | 1.04 (1.01, 1.06) | NA
Velpatasvir | 100 once daily | 25 once daily | 30 | 1.05 (0.96, 1.16) | 1.01 (0.94, 1.07) | 1.01 (0.95,1.09)
Voxilaprevir | 100 + 100 once daily | 25 once daily | 30 | 0.96 (0.84, 1.11) | 0.94 (0.84, 1.05) | 1.02 (0.92,1.12)
CI=Confidence Interval; N=maximum number of participants with data; NA=Not Available

12.4 Microbiology

Mechanism of Action

Emtricitabine: FTC, a synthetic nucleoside analog of cytidine, is phosphorylated by cellular enzymes to form emtricitabine 5'-triphosphate. Emtricitabine 5'-triphosphate inhibits the activity of the HIV-1 reverse transcriptase (RT) by competing with the natural substrate deoxycytidine 5'-triphosphate and by being incorporated into nascent viral DNA which results in chain termination. Emtricitabine 5′-triphosphate is a weak inhibitor of mammalian DNA polymerases α, β, Ɛ, and mitochondrial DNA polymerase γ.

Rilpivirine: RPV is a diarylpyrimidine non-nucleoside reverse transcriptase inhibitor of HIV-1 and inhibits HIV-1 replication by non-competitive inhibition of HIV-1 RT. RPV does not inhibit the human cellular DNA polymerases α, β, and mitochondrial DNA polymerase γ.

Tenofovir Alafenamide: TAF is a phosphonamidate prodrug of tenofovir (2'-deoxyadenosine monophosphate analog). Plasma exposure to TAF allows for permeation into cells and then TAF is intracellularly converted to tenofovir through hydrolysis by cathepsin A. Tenofovir is subsequently phosphorylated by cellular kinases to the active metabolite tenofovir diphosphate. Tenofovir diphosphate inhibits HIV-1 replication through incorporation into viral DNA by the HIV reverse transcriptase, which results in DNA chain termination.

Tenofovir has activity against human immunodeficiency virus (HIV-1). Cell culture studies have shown that both tenofovir and FTC can be fully phosphorylated when combined in cells. Tenofovir diphosphate is a weak inhibitor of mammalian DNA polymerases that include mitochondrial DNA polymerase γ and there is no evidence of toxicity to mitochondria cell culture.

Antiviral Activity in Cell Culture

Emtricitabine, Rilpivirine, and Tenofovir Alafenamide: The combinations of FTC, RPV, and TAF were not antagonistic with each other in cell culture combination antiviral activity assays. In addition, FTC, RPV, and TAF were not antagonistic with a panel of representatives from the major classes of approved anti-HIV agents (NNRTIs, NRTIs, INSTIs, and PIs).

Emtricitabine: The antiviral activity of FTC against laboratory and clinical isolates of HIV-1 was assessed in T lymphoblastoid cell lines, the MAGI-CCR5 cell line, and primary peripheral blood mononuclear cells (PBMCs). The EC50 values for FTC were in the range of 1.3–640 nM. FTC displayed antiviral activity in cell culture against HIV-1 clades A, B, C, D, E, F, and G (EC50 values ranged from 7–75 nM) and showed strain-specific activity against HIV-2 (EC50 values ranged from 7–1500 nM).

Rilpivirine: RPV exhibited activity against laboratory strains of wild-type HIV-1 in an acutely infected T-cell line with a median EC50 value for HIV-1IIIB of 0.73 nM. RPV demonstrated limited activity in cell culture against HIV-2 with a median EC50 value of 5220 nM (range 2510–10,830 nM). RPV demonstrated antiviral activity against a broad panel of HIV-1 group M (subtype A, B, C, D, F, G, H) primary isolates with EC50 values ranging from 0.07–1.01 nM and was less active against group O primary isolates with EC50 values ranging from 2.88–8.45 nM.

Tenofovir Alafenamide: The antiviral activity of TAF against laboratory and clinical isolates of HIV-1 subtype B was assessed in lymphoblastoid cell lines, PBMCs, primary monocyte/macrophage cells and CD4-T lymphocytes. The EC50 values for TAF ranged from 2.0–14.7 nM.

TAF displayed antiviral activity in cell culture against all HIV-1 groups (M, N, O), including sub-types A, B, C, D, E, F, and G (EC50 values ranged from 0.10–12.0 nM) and strain specific activity against HIV-2 (EC50 values ranged from 0.91–2.63 nM).

Resistance

In Cell Culture

Emtricitabine: HIV-1 isolates with reduced susceptibility to FTC were selected in cell culture. Reduced susceptibility to FTC was associated with M184V or I substitutions in HIV-1 RT.

Rilpivirine: RPV-resistant strains were selected in cell culture starting from wild-type HIV-1 of different origins and subtypes as well as NNRTI-resistant HIV-1. The frequently observed amino acid substitutions that emerged and conferred decreased phenotypic susceptibility to RPV included: L100I, K101E, V106I and A, V108I, E138K and G, Q, R, V179F and I, Y181C and I, V189I, G190E, H221Y, F227C, and M230I and L.

Tenofovir Alafenamide: HIV-1 isolates with reduced susceptibility to TAF were selected in cell culture. HIV-1 isolates selected by TAF expressed a K65R substitution in HIV-1 RT, sometimes in the presence of S68N or L429I substitutions; in addition, a K70E substitution in HIV-1 RT was observed.

In Clinical Trials

In Participants With HIV-1 and No Antiretroviral Treatment History

Emtricitabine and Tenofovir Alafenamide: The resistance profile of ODEFSEY for the treatment of HIV-1 is based on studies of FTC+TAF with EVG+COBI in the treatment of HIV-1. In a pooled analysis of antiretroviral-naïve participants, genotyping was performed on plasma HIV-1 isolates from all participants with HIV-1 RNA greater than 400 copies per mL at confirmed virologic failure, at Week 48, or at time of early study drug discontinuation. Genotypic resistance developed in 7 of 14 evaluable participants. The resistance–associated substitutions that emerged were M184V/I (N=7) and K65R (N=1). Three participants had virus with emergent R, H, or E at the polymorphic Q207 residue in reverse transcriptase.

Rilpivirine: In the Week 96 pooled resistance analysis for adult participants receiving RPV or efavirenz in combination with FTC/TDF, the emergence of resistance was greater among participants' viruses in the RPV+FTC/TDF arm compared to the efavirenz+FTC/TDF arm and was dependent on baseline viral load. In the Week 96 resistance analysis, 14% (77/550) of the participants in the RPV+FTC/TDF arm and 8% (43/546) of the participants in the efavirenz+FTC/TDF arm qualified for resistance analysis; 61% (47/77) of the participants who qualified for resistance analysis (resistance-analysis participants) in the RPV+FTC/TDF arm had virus with genotypic and/or phenotypic resistance to RPV compared to 42% (18/43) of the resistance-analysis participants in the efavirenz+FTC/TDF arm who had genotypic and/or phenotypic resistance to efavirenz. Moreover, genotypic and/or phenotypic resistance to emtricitabine or tenofovir emerged in viruses from 57% (44/77) of the resistance-analysis participants in the RPV arm compared to 26% (11/43) in the efavirenz arm.

Emerging NNRTI substitutions in the RPV resistance analysis of participants' viruses included V90I, K101E/P/T, E138K/A/Q/G, V179I/L, Y181C/I, V189I, H221Y, F227C/L, and M230L, which were associated with an RPV phenotypic fold change range of 2.6–621. The E138K substitution emerged most frequently during RPV treatment, commonly in combination with the M184I substitution. The emtricitabine and lamivudine resistance-associated substitutions M184I or V and NRTI resistance-associated substitutions (A62V, K65R/N, D67N/G, K70E, Y115F, K219E/R) emerged more frequently in the RPV resistance-analysis participants than in efavirenz resistance-analysis participants.

NNRTI- and NRTI-resistance substitutions emerged less frequently in the resistance analysis of viruses from participants with baseline viral loads of less than or equal to 100,000 copies/mL compared to viruses from participants with baseline viral loads of greater than 100,000 copies/mL: 23% (10/44) compared to 77% (34/44) of NNRTI-resistance substitutions and 20% (9/44) compared to 80% (35/44) of NRTI-resistance substitutions. This difference was also observed for the individual emtricitabine/lamivudine and tenofovir resistance substitutions: 22% (9/41) compared to 78% (32/41) for M184I/V and 0% (0/8) compared to 100% (8/8) for K65R/N. Additionally, NNRTI and/or NRTI-resistance substitutions emerged less frequently in the resistance analysis of the viruses from participants with baseline CD4+ cell counts greater than or equal to 200 cells/mm^3 compared to the viruses from participants with baseline CD4+ cell counts less than 200 cells/mm^3: 32% (14/44) compared to 68% (30/44) of NNRTI-resistance substitutions and 27% (12/44) compared to 73% (32/44) of NRTI-resistance substitutions.

In Virologically-Suppressed Participants

Emtricitabine and Tenofovir Alafenamide: One participant was identified with emergent resistance to FTC or TAF (M184M/I) out of 4 virologic failure participants in a clinical study of virologically-suppressed participants who switched from a regimen containing FTC+TDF to FTC+TAF with EVG+COBI (N=799).

Rilpivirine: Through Week 48, 4 participants who switched their protease inhibitor-based regimen to FTC/RPV/TDF (4 of 469 participants, 0.9%) and 1 participant who maintained their regimen (1 of 159 participants, 0.6%) developed genotypic and/or phenotypic resistance to a study drug. All 4 of the participants who had resistance emergence on FTC/RPV/TDF had evidence of FTC resistance and 3 of the participants had evidence of RPV resistance.

ODEFSEY: Through Week 48, in participants who switched to ODEFSEY from FTC/RPV/TDF or EFV/FTC/TDF (Trials 1216 (N=316) and 1160 (N=438), respectively), of seven participants who developed virologic failure, three participants had detectable NNRTI and/or NRTI resistance substitutions at virologic failure that were pre-existing in the baseline sample by proviral DNA sequencing; one of these participants resuppressed while maintaining ODEFSEY.

Cross-Resistance

Emtricitabine: FTC-resistant viruses with the M184V/I substitution were cross-resistant to lamivudine, but retained sensitivity to didanosine, stavudine, tenofovir, and zidovudine.

Viruses harboring substitutions conferring reduced susceptibility to stavudine and zidovudine—thymidine analog substitutions (M41L, D67N, K70R, L210W, T215Y/F, K219Q/E), or didanosine (L74V) remained sensitive to FTC. HIV-1 containing the K103N substitution or other substitutions associated with resistance to NNRTIs was susceptible to FTC.

Rilpivirine: Considering all of the available cell culture and clinical data, any of the following amino acid substitutions, when present at baseline, are likely to decrease the antiviral activity of RPV: K101E, K101P, E138A, E138G, E138K, E138R, E138Q, V179L, Y181C, Y181I, Y181V, Y188L, H221Y, F227C, M230I, M230L, and the combination of L100I+K103N.

Cross-resistance in site-directed mutant virus has been observed among NNRTIs. The single NNRTI substitutions K101P, Y181I, and Y181V conferred 52 times, 15 times, and 12 times decreased susceptibility to RPV, respectively. The combination of E138K and M184I showed 6.7 times reduced susceptibility to RPV compared to 2.8 times for E138K alone. The K103N substitution did not show reduced susceptibility to RPV by itself. However, the combination of L100I and K103N resulted in a 7 times reduced susceptibility to RPV. In another study, the Y188L substitution resulted in a reduced susceptibility to RPV of 9 times for clinical isolates and 6 times for site-directed mutants. Combinations of 2 or 3 NNRTI resistance-associated substitutions gave decreased susceptibility to RPV (fold change range of 3.7–554) in 38% and 66% of mutants, respectively.

Cross-resistance to efavirenz, etravirine, and/or nevirapine is likely after virologic failure and development of RPV resistance.

Tenofovir Alafenamide: Tenofovir resistance substitutions K65R and K70E result in reduced susceptibility to abacavir, didanosine, emtricitabine, lamivudine, and tenofovir.

HIV-1 with multiple thymidine analog substitutions (M41L, D67N, K70R, L210W, T215F/Y, K219Q/E/N/R), or multinucleoside resistant HIV-1 with a T69S double insertion mutation or with a Q151M substitution complex including K65R showed reduced susceptibility to TAF in cell culture.

13 NONCLINICAL TOXICOLOGY

13.1 Carcinogenesis, Mutagenesis, Impairment of Fertility

Emtricitabine: In long-term carcinogenicity studies of FTC, no drug-related increases in tumor incidence were found in mice at doses up to 750 mg per kg per day (23 times the human systemic exposure at the recommended dose of 200 mg per day in ODEFSEY) or in rats at doses up to 600 mg per kg per day (28 times the human systemic exposure at the recommended dose in ODEFSEY).

FTC was not genotoxic in the reverse mutation bacterial test (Ames test), mouse lymphoma or mouse micronucleus assays.

FTC did not affect fertility in male rats at approximately 140 times or in male and female mice at approximately 60 times higher exposures (AUC) than in humans given the recommended 200 mg daily dose in ODEFSEY. Fertility was normal in the offspring of mice exposed daily from before birth (in utero) through sexual maturity at daily exposures (AUC) of approximately 60 times higher than human exposures at the recommended 200 mg daily dose in ODEFSEY.

Rilpivirine: RPV was evaluated for carcinogenic potential by oral gavage administration to mice and rats up to 104 weeks. Daily doses of 20, 60, and 160 mg per kg per day were administered to mice and doses of 40, 200, 500, and 1500 mg per kg per day were administered to rats. In rats, there were no drug-related neoplasms. In mice, RPV was positive for hepatocellular neoplasms in both males and females. The observed hepatocellular findings in mice may be rodent-specific. At the lowest tested doses in the carcinogenicity studies, the systemic exposures (based on AUC) to RPV were 21 times (mice) and 3 times (rats) relative to those observed in humans at the recommended dose (25 mg once daily) in ODEFSEY.

RPV has tested negative in the absence and presence of a metabolic activation system, in the in vitro Ames reverse mutation assay and in vitro clastogenicity mouse lymphoma assay. RPV did not induce chromosomal damage in the in vivo micronucleus test in mice.

In a study conducted in rats, there were no effects on mating or fertility with RPV up to 400 mg per kg per day, a dose of RPV that showed maternal toxicity. This dose is associated with an exposure that is approximately 40 times higher than the exposure in humans at the recommended dose of 25 mg once daily in ODEFSEY.

Tenofovir Alafenamide: Since TAF is rapidly converted to tenofovir and a lower tenofovir exposure in rats and mice was observed after TAF administration compared to TDF administration, carcinogenicity studies were conducted only with TDF. Long-term oral carcinogenicity studies of TDF in mice and rats were carried out at exposures up to approximately 10 times (mice) and 4 times (rats) those observed in humans at the recommended dose of TDF (300 mg) for HIV-1 infection. The tenofovir exposure in these studies was approximately 167 times (mice) and 55 times (rat) those observed in humans after administration of the daily recommended dose of ODEFSEY. At the high dose in female mice, liver adenomas were increased at tenofovir exposures approximately 10 times (300 mg TDF) and 167 times (ODEFSEY) the exposure observed in humans. In rats, the study was negative for carcinogenic findings.

TAF was not genotoxic in the reverse mutation bacterial test (Ames test), mouse lymphoma or rat micronucleus assays.

There were no effects on fertility, mating performance or early embryonic development when TAF was administered to male rats at a dose equivalent to 62 times the human dose based on body surface area comparisons for 28 days prior to mating and to female rats for 14 days prior to mating through Day 7 of gestation.

13.2 Animal Toxicology and/or Pharmacology

Minimal to slight infiltration of mononuclear cells in the posterior uvea was observed in dogs with similar severity after three- and nine-month administration of TAF; reversibility was seen after a three-month recovery period. No eye toxicity was observed in the dog at systemic exposures of 5 (TAF) and 15 (tenofovir) times the exposure seen in humans at the recommended daily TAF dose in ODEFSEY.

14 CLINICAL STUDIES

14.1 Clinical Trial Results in HIV-1 Virologically-Suppressed Subjects Who Switched to ODEFSEY

In Trial 1216, the efficacy and safety of switching from emtricitabine/rilpivirine/tenofovir disoproxil fumarate (FTC/RPV/TDF) to ODEFSEY were evaluated in a randomized, double-blind study of virologically-suppressed adults with HIV-1. Participants were suppressed (HIV-1 RNA <50 copies/mL) on their baseline regimen of FTC/RPV/TDF for at least 6 months and had no documented resistance mutations to FTC, TAF, or RPV prior to study entry. Participants were randomized in a 1:1 ratio to either switch to ODEFSEY (N=316) once daily or stay on FTC/RPV/TDF (N=314) once daily. Participants had a mean age of 45 years (range: 23–72), 90% were male, 75% were White, and 19% were Black. The mean baseline CD4+ cell count was 709 cells/mm^3 (range: 104–2527).

In Trial 1160, the efficacy and safety of switching from efavirenz/emtricitabine/tenofovir disoproxil fumarate (EFV/FTC/TDF) to ODEFSEY were evaluated in a randomized, double-blind study of virologically-suppressed adults with HIV-1. Participants were stably suppressed (HIV-1 RNA <50 copies/mL) on their baseline regimen of EFV/FTC/TDF for at least 6 months and had no documented resistance mutations to FTC, TAF, or RPV prior to study entry. Participants were randomized in a 1:1 ratio to either switch to ODEFSEY (N=438) once daily or stay on EFV/FTC/TDF (N=437) once daily. Participants had a mean age of 48 years (range: 19–76), 87% were male, 67% were White, and 27% were Black. The mean baseline CD4+ cell count was 700 cells/mm^3 (range: 140–1862).

Treatment outcomes of Trials 1216 and 1160 are presented in Table 13.

Table 13 Virologic Outcomes of Trials 1216 and 1160 at Week 48 [Week 48 window was between Day 295 and 378 (inclusive).] in Virologically-Suppressed Participants who Switched to ODEFSEY
 | Study 1216 |  | Study 1160
 | ODEFSEY (N=316) | FTC/RPV/TDF (N=313) [One subject who was not on FTC/RPV/TDF prior to screening was excluded from the efficacy analysis.] | ODEFSEY (N=438) | EFV/FTC/TDF (N=437)
HIV-1 RNA <50 copies/mL | 94% | 94% | 90% | 92%
HIV-1 RNA ≥50 copies/mL [Included participants who had HIV-1 RNA ≥50 copies/mL in the Week 48 window; participants who discontinued early due to lack or loss of efficacy; participants who discontinued for reasons other than lack or loss of efficacy and at the time of discontinuation had a viral value of ≥50 copies/mL.] | 1% | 0% | 1% | 1%
No Virologic Data at Week 48 Window | 6% | 6% | 9% | 7%
Discontinued Study Drug Due to AE or Death and Last Available HIV-1 RNA <50 copies/mL | 2% | 1% | 3% | 1%
Discontinued Study Drug Due to Other Reasons and Last Available HIV-1 RNA <50 copies/mL [Includes participants who discontinued for reasons other than an AE, death, or lack or loss of efficacy; e.g., withdrew consent, loss to follow-up, etc.] | 4% | 4% | 5% | 5%
Missing Data During Window but on Study Drug | <1% | 1% | 1% | 1%

14.2 Clinical Trial Results for Adult Participants with no Antiretroviral Treatment History and Adults with Renal Impairment for Components of ODEFSEY

The efficacy of RPV, FTC, and TAF in the treatment of HIV-1 infection in adults as initial therapy in those with no antiretroviral treatment history [see Indications and Usage (1)] was established in trials of:

- RPV+FTC/TDF in adults with HIV-1 as initial therapy in those with no antiretroviral treatment history (n=550). The virologic response rate (i.e., HIV-1 RNA less than 50 copies per mL) was 77% at Week 96. The virologic response rate at 96 weeks was 83% in participants with baseline HIV-1 RNA less than or equal to 100,000 copies per mL and 71% in participants with baseline HIV-1 RNA greater than 100,000 copies per mL. Further, the virologic response rate at 96 weeks among participants with baseline CD4+ cell counts less than 200 and greater than or equal to 200 cells/mm^3 were 68% and 82%, respectively.
- FTC+TAF with EVG+COBI in adults with HIV-1 as initial therapy in those with no antiretroviral treatment history (n=866). The virologic response rate (i.e., HIV-1 RNA less than 50 copies per mL) was 92% at Week 48.

In the clinical trial of 248 adults with HIV-1 and estimated creatinine clearance greater than 30 mL per minute but less than 70 mL per minute, 95% (235/248) of the combined populations of treatment-naïve (N=6) begun on FTC+TAF with EVG+COBI and those previously virologically-suppressed on other regimens (N=242) and switched to FTC+TAF with EVG +COBI had HIV-1 RNA levels less than 50 copies per mL at Week 24.

14.3 Clinical Trial Results for Pediatric Participants Aged 6 to Less than 18 Years Old for Components of ODEFSEY

The efficacy of RPV, FTC, and TAF in the treatment of HIV-1 infection in pediatric patients aged 6 to less than 18 years old and greater than 25 kg as initial therapy in those with no antiretroviral treatment history and to replace a stable antiretroviral regimen in those who are virologically-suppressed [see Indications and Usage (1)] was established in trials of pediatric participants with HIV-1 aged 6 to less than 18 years with:

- RPV in combination with other antiretroviral agents in 36 treatment-naïve adolescents with HIV-1 weighing at least 32 kg. The majority of participants (24/36) received RPV in combination with FTC and TDF. Of these 24 participants, 20 had a baseline HIV-1 RNA less than or equal to 100,000 copies per mL. The virologic response rate in these 20 participants (i.e., HIV-1 RNA less than 50 copies per mL) was 80% (16/20) at 48 weeks.
- RPV in combination with other antiretroviral agents (two NRTIs) in 18 treatment-naïve pediatric participants with HIV-1 weighing at least 17 kg (median [range]: 25 kg [17–51 kg]). The virologic response rate (i.e., HIV-1 RNA less than 50 copies per mL) was 72% (13/18) at 48 weeks.
- RPV in combination with other antiretrovirals in 26 virologically-suppressed pediatric participants with HIV-1 less than 12 years old weighing at least 16 kg (N=26) at 48-week.
- FTC+TAF with EVG+COBI in 50 treatment-naïve adolescents with HIV-1 aged 12 to less than 18 years weighing at least 35 kg. The virologic response rate (i.e., HIV-1 RNA less than 50 copies per mL) was 92% (46/50) at 48 weeks.
- FTC+TAF with EVG+COBI in 52 virologically-suppressed pediatric participants with HIV-1 aged 6 to less than 12 years weighing at least 25 kg. The virologic response rate (i.e., HIV-1 RNA less than 50 copies per mL) was 98% (51/52) at 48 weeks.

16 HOW SUPPLIED/STORAGE AND HANDLING

ODEFSEY tablets are gray, capsule-shaped, and film coated with "GSI" debossed on one side and "255" on the other side. Each bottle contains 30 tablets (NDC 61958-2101-1), a silica gel desiccant, and a polyester coil, and is closed with a child-resistant closure.

STORAGE AND HANDLING

Store below 30°C (86°F).

- Keep container tightly closed.
- Dispense only in original container.

17 PATIENT COUNSELING INFORMATION

Advise the patient to read the FDA-approved patient labeling (Patient Information).

Post-treatment Acute Exacerbation of Hepatitis B in Patients with HBV Coinfection

Severe acute exacerbations of hepatitis B have been reported in patients with HBV and HIV-1 who have discontinued products containing FTC and/or TDF, and may likewise occur with discontinuation of ODEFSEY [see Warnings and Precautions (5.1)]. Advise the patient to not discontinue ODEFSEY without first informing their healthcare provider.

Severe Skin Reactions and Hypersensitivity

Inform patients that skin reactions ranging from mild to severe, including Drug Reaction with Eosinophilia and Systemic Symptoms (DRESS), have been reported with RPV-containing products. Instruct patients to immediately stop taking ODEFSEY and seek medical attention if they develop a rash associated with any of the following symptoms: fever, blisters, mucosal involvement, eye inflammation (conjunctivitis), severe allergic reaction causing swelling of the face, eyes, lips, mouth, tongue or throat which may lead to difficulty swallowing or breathing, and any signs and symptoms of liver problems, as they may be a sign of a more serious reaction. Patients should understand that if severe rash occurs, they will be closely monitored, laboratory tests will be performed and appropriate therapy will be initiated [see Warnings and Precautions (5.2)].

Hepatotoxicity

Inform patients that hepatotoxicity has been reported with RPV, therefore, it is important to inform the healthcare professional if patients have underlying hepatitis B or C or elevations in liver-associated tests prior to treatment [see Dosage and Administration (2.1) and Warnings and Precautions (5.3)].

Depressive Disorders

Inform patients that depressive disorders (depressed mood, depression, dysphoria, major depression, mood altered, negative thoughts, suicide attempt, suicidal ideation) have been reported with RPV. Inform patients to seek immediate medical evaluation if they experience depressive symptoms [see Warnings and Precautions (5.4)].

New Onset or Worsening Renal Impairment

Advise patients to avoid taking ODEFSEY with concurrent or recent use of nephrotoxic agents. Postmarketing cases of renal impairment, including acute renal failure, have been reported [see Warnings and Precautions (5.5)].

Drug Interactions

ODEFSEY may interact with many drugs and is not recommended to be coadministered with numerous drugs. Advise patients to report to their healthcare provider the use of any other prescription or nonprescription medication or herbal products, including St. John's wort [see Contraindications (4), Warnings and Precautions (5.6) and Drug Interactions (7)].

Lactic Acidosis and Severe Hepatomegaly

Lactic acidosis and severe hepatomegaly with steatosis, including fatal cases, have been reported with use of drugs similar to ODEFSEY. Advise patients to stop taking ODEFSEY if they develop clinical symptoms suggestive of lactic acidosis or pronounced hepatotoxicity [see Warnings and Precautions (5.7)].

Immune Reconstitution Syndrome

Advise patients to inform their healthcare provider immediately of any symptoms of infection, as in some patients with advanced HIV infection (AIDS), signs and symptoms of inflammation from previous infections may occur soon after anti-HIV treatment is started [see Warnings and Precautions (5.8)].

Missed Dosage

Inform patients that it is important to take ODEFSEY on a regular dosing schedule with a meal and to avoid missing doses, as it can result in development of resistance [see Dosage and Administration (2.2)].

Pregnancy Registry

Inform patients that there is an antiretroviral pregnancy registry to monitor fetal outcomes in those exposed to ODEFSEY during pregnancy [see Use in Specific Populations (8.1)].

Lactation

Instruct patients with HIV-1 that the potential risks of breastfeeding include: (1) HIV-1 transmission to infants without HIV-1, (2) developing viral resistance in infants with HIV-1, and (3) adverse reactions in a breastfed infant similar to those seen in adults [see Use in Specific Populations (8.2)].

ODEFSEY is a trademark of Gilead Sciences, Inc., or its related companies. All other trademarks referenced herein are the property of their respective owners.

Patient Information
ODEFSEY® (oh-DEF-see)
(emtricitabine, rilpivirine and tenofovir alafenamide)
tablets

Important: Ask your healthcare provider or pharmacist about medicines that should not be taken with ODEFSEY. For more information, see "What should I tell my healthcare provider before taking ODEFSEY?"

What is the most important information I should know about ODEFSEY?
ODEFSEY can cause serious side effects, including:

- Worsening of hepatitis B virus (HBV) infection. Your healthcare provider will test you for HBV before or when you start treatment with ODEFSEY. If you have HBV and take ODEFSEY, your HBV may get worse (flare-up) if you stop taking ODEFSEY. A "flare-up" is when your HBV suddenly returns in a worse way than before.
  - Do not run out of ODEFSEY. Refill your prescription or talk to your healthcare provider before your ODEFSEY is all gone.
  - Do not stop taking ODEFSEY without first talking to your healthcare provider.
  - If you stop taking ODEFSEY, your healthcare provider will need to check your health often and do blood tests regularly for several months to check your liver, and may give you a medicine to treat hepatitis B. Tell your healthcare provider about any new or unusual symptoms you may have after you stop taking ODEFSEY.

For more information about side effects, see "What are the possible side effects of ODEFSEY?"

What is ODEFSEY?
ODEFSEY is a prescription medicine that is used to treat human immunodeficiency virus-1 (HIV-1) infection in adults and children who weigh at least 55 pounds (25 kg):

- who have not received HIV-1 medicines in the past and who have an amount of HIV-1 in their blood (this is called "viral load") that is no more than 100,000 copies/mL, or
- to replace their current HIV-1 medicines for people whose healthcare provider determines that they meet certain requirements.

HIV-1 is the virus that causes Acquired Immune Deficiency Syndrome (AIDS).
ODEFSEY contains the prescription medicines emtricitabine, rilpivirine and tenofovir alafenamide.
It is not known if ODEFSEY is safe and effective in children who weigh less than 55 pounds (25 kg).

Who should not take ODEFSEY?
Do not take ODEFSEY if you also take a medicine that contains:

- carbamazepine
- dexamethasone
- dexlansoprazole
- esomeprazole
- lansoprazole
- omeprazole
- oxcarbazepine
- pantoprazole sodium

- phenobarbital
- phenytoin
- rabeprazole
- rifampin
- rifapentine
- St. John's wort (Hypericum perforatum) or a product that contains St. John's wort

What should I tell my healthcare provider before taking ODEFSEY?
Before taking ODEFSEY, tell your healthcare provider about all of your medical conditions, including if you:

- have liver problems, including HBV or hepatitis C virus
- have kidney problems
- have a history of depression or suicidal thoughts
- are pregnant or plan to become pregnant. It is not known if ODEFSEY can harm your unborn baby. Tell your healthcare provider if you become pregnant during treatment with ODEFSEY.
  Pregnancy Registry: There is a pregnancy registry for those who take ODEFSEY during pregnancy. The purpose of this registry is to collect information about the health of you and your baby. Talk with your healthcare provider about how you can take part in this registry.
- are breastfeeding or plan to breastfeed.
  - Two of the medicines in ODEFSEY can pass to your baby in your breast milk. It is not known if the other medicine in ODEFSEY can pass into your breast milk.
  - Talk to your healthcare provider about the following risks of breastfeeding during treatment with ODEFSEY:
    - The HIV-1 virus may pass to your baby if your baby does not have HIV-1.
    - The HIV-1 virus may become harder to treat if your baby has HIV-1.
    - Your baby may get side effects from ODEFSEY.

Tell your healthcare provider about all the medicines you take, including prescription and over-the-counter medicines, vitamins, and herbal supplements.
Some medicines may interact with ODEFSEY. Keep a list of your medicines and show it to your healthcare provider and pharmacist when you get a new medicine.

- You can ask your healthcare provider or pharmacist for a list of medicines that interact with ODEFSEY.
- Do not start a new medicine without telling your healthcare provider. Your healthcare provider can tell you if it is safe to take ODEFSEY with other medicines.

How should I take ODEFSEY?

- Take ODEFSEY exactly as your healthcare provider tells you to take it. ODEFSEY is taken by itself (not with other HIV-1 medicines) to treat HIV-1 infection.
- Take ODEFSEY 1 time each day with a meal.
- If you are on dialysis, take your daily dose of ODEFSEY following dialysis.
- Do not change your dose or stop taking ODEFSEY without first talking with your healthcare provider. Stay under a healthcare provider's care during treatment with ODEFSEY.
- Do not miss a dose of ODEFSEY.
- When your ODEFSEY supply starts to run low, get more from your healthcare provider or pharmacy. This is very important because the amount of virus in your blood may increase if the medicine is stopped for even a short time. The virus may develop resistance to ODEFSEY and become harder to treat.
- If you take too much ODEFSEY, call your healthcare provider or go to the nearest hospital emergency room right away.

What are the possible side effects of ODEFSEY?
ODEFSEY may cause serious side effects, including:

- See "What is the most important information I should know about ODEFSEY?"
- Severe skin rash and allergic reactions. Skin rash is a common side effect of ODEFSEY. Rash can be serious. Call your healthcare provider right away if you get a rash. In some cases, rash and allergic reaction may need to be treated in a hospital.
  If you get a rash with any of the following symptoms, stop taking ODEFSEY and call your healthcare provider or get medical help right away:

- fever
- skin blisters
- mouth sores
- redness or swelling of the eyes (conjunctivitis)

- swelling of the face, lips, mouth, or throat
- trouble breathing or swallowing
- pain on the right side of the stomach (abdominal) area
- dark "tea colored" urine

- Change in liver enzymes. People with a history of hepatitis B or C virus or who have certain liver enzyme changes may have an increased risk of developing new or worsening liver problems during treatment with ODEFSEY. Liver problems can also happen during treatment with ODEFSEY in people without a history of liver disease. Your healthcare provider may need to do tests to check your liver enzymes before and during treatment with ODEFSEY.
- Depression or mood changes. Tell your healthcare provider right away if you have any of the following symptoms:
  - feel sad or hopeless
  - feel anxious or restless
  - have thoughts of hurting yourself (suicide) or have tried to hurt yourself
- New or worse kidney problems, including kidney failure. Your healthcare provider should do blood and urine tests to check your kidneys before you start and during treatment with ODEFSEY. Your healthcare provider may tell you to stop taking ODEFSEY if you develop new or worse kidney problems.
- Too much lactic acid in your blood (lactic acidosis). Too much lactic acid is a serious but rare medical emergency that can lead to death. Tell your healthcare provider right away if you get these symptoms: weakness or being more tired than usual, unusual muscle pain, being short of breath or fast breathing, stomach pain with nausea and vomiting, cold or blue hands and feet, feel dizzy or lightheaded, or a fast or abnormal heartbeat.
- Severe liver problems. In rare cases, severe liver problems can happen that can lead to death. Tell your healthcare provider right away if you get these symptoms: skin or the white part of your eyes turns yellow, dark "tea-colored" urine, light-colored stools, loss of appetite for several days or longer, nausea, or stomach-area pain.
- Changes in your immune system (Immune Reconstitution Syndrome) can happen when you start taking HIV-1 medicines. Your immune system may get stronger and begin to fight infections that have been hidden in your body for a long time. Tell your healthcare provider right away if you start having any new symptoms after starting your HIV-1 medicine.

The most common side effects of ODEFSEY are headache and problems sleeping.
These are not all of the possible side effects of ODEFSEY.
Call your doctor for medical advice about side effects. You may report side effects to FDA at 1-800-FDA-1088.

How should I store ODEFSEY?

- Store ODEFSEY below 86°F (30°C).
- Keep ODEFSEY in its original container.
- Keep the container tightly closed.

Keep ODEFSEY and all medicines out of the reach of children.

General information about the safe and effective use of ODEFSEY.
Medicines are sometimes prescribed for purposes other than those listed in a Patient Information leaflet. Do not use ODEFSEY for a condition for which it was not prescribed. Do not give ODEFSEY to other people, even if they have the same symptoms you have. It may harm them. You can ask your healthcare provider or pharmacist for information about ODEFSEY that is written for health professionals.

What are the ingredients in ODEFSEY?
Active ingredients: emtricitabine, rilpivirine, and tenofovir alafenamide.
Inactive ingredients: croscarmellose sodium, lactose monohydrate, magnesium stearate, microcrystalline cellulose, polysorbate 20, and povidone. The tablet film coating contains iron oxide black, polyethylene glycol, polyvinyl alcohol, talc, and titanium dioxide.
Manufactured and distributed by: Gilead Sciences, Inc. Foster City, CA 94404
ODEFSEY is a trademark of Gilead Sciences, Inc., or its related companies.
© 2025 Gilead Sciences, Inc. All rights reserved. 208351-GS-007
For more information, call 1-800-445-3235 or go to www.ODEFSEY.com.

This Patient Information has been approved by the U.S. Food and Drug Administration

Revised: 02/2025

PRINCIPAL DISPLAY PANEL - 30 Tablet Bottle Label

NDC 61958- 2101-1
30 tablets

Odefsey ®
(emtricitabine, rilpivirine, and
tenofovir alafenamide) Tablets
200 mg/25 mg/25 mg

Note to pharmacist:
Do not cover ALERT box with pharmacy label.

ALERT: Find out about medicines that
should NOT be taken with Odefsey ®